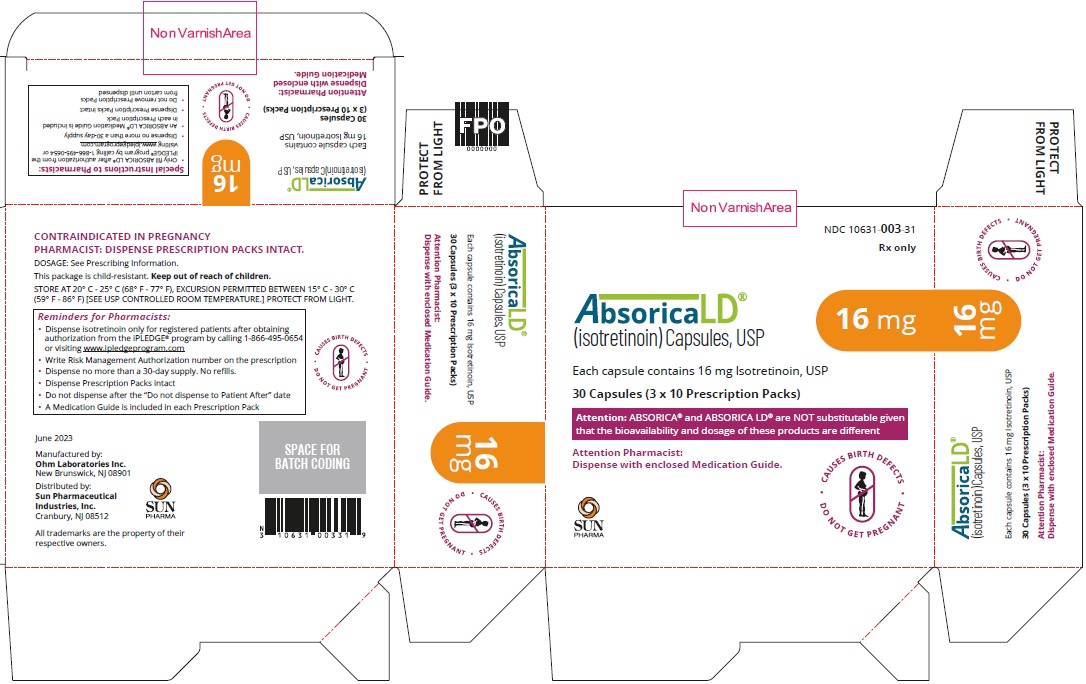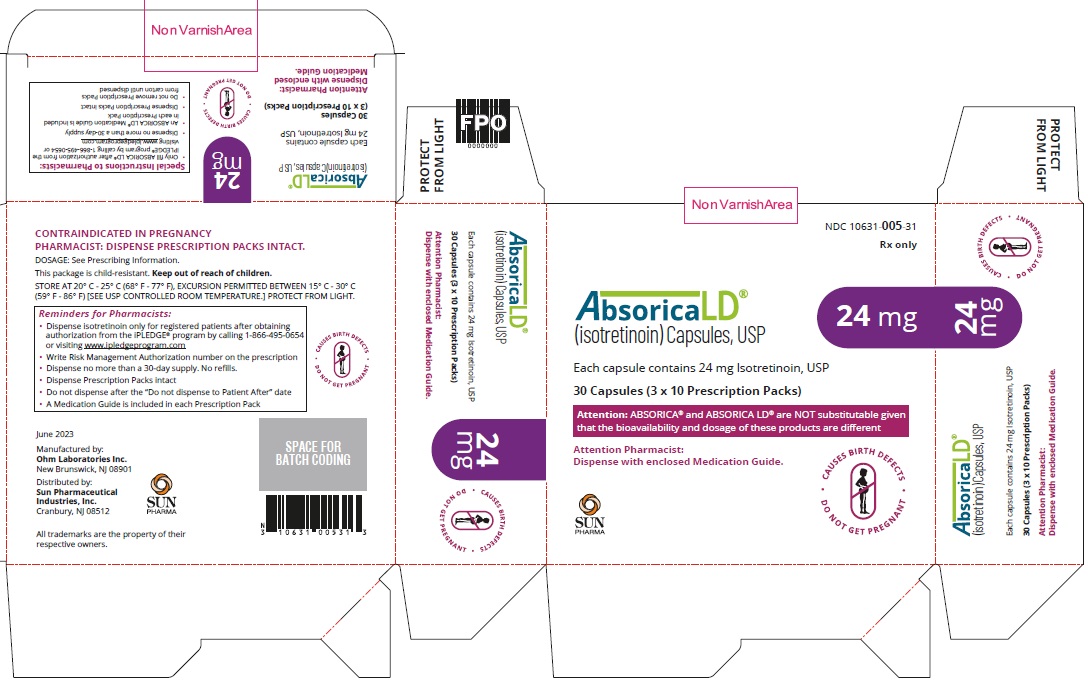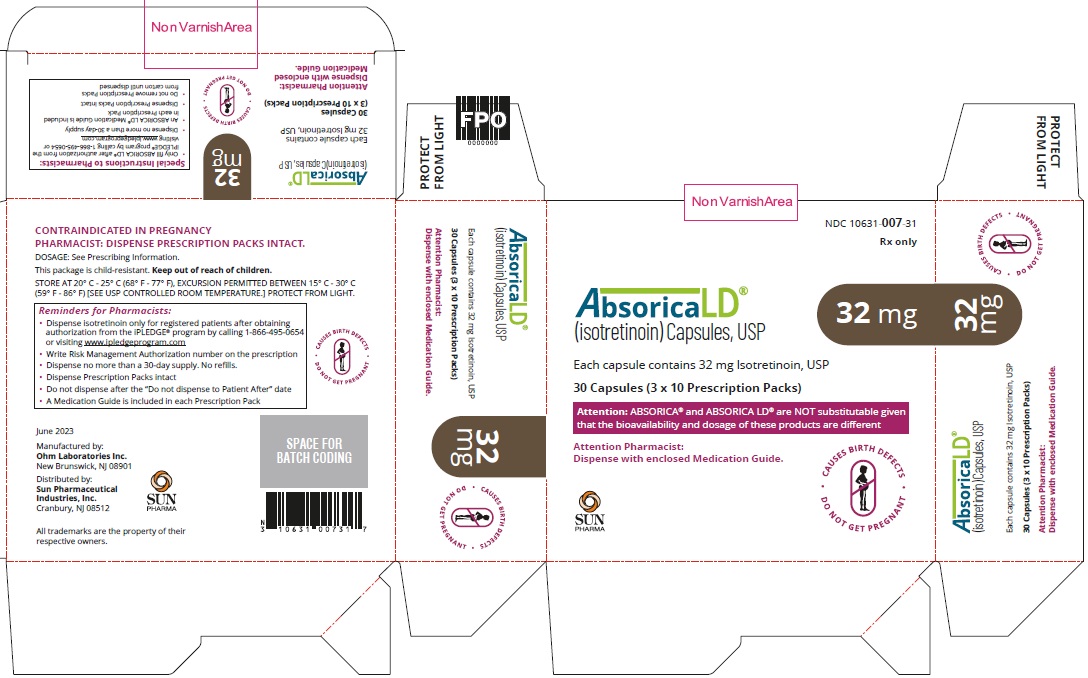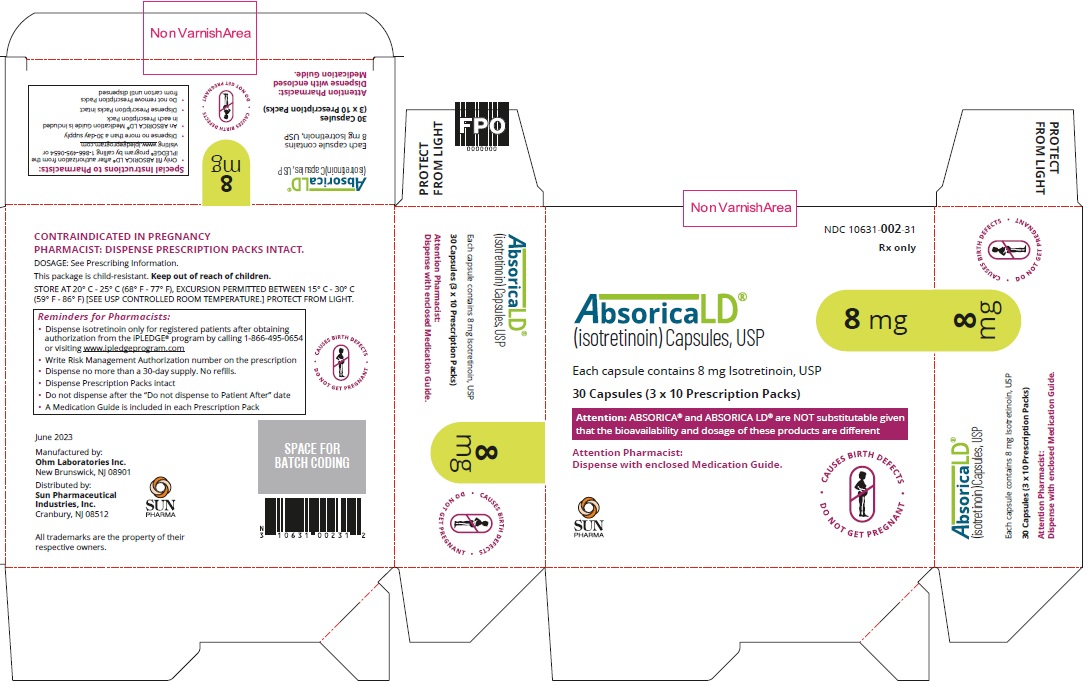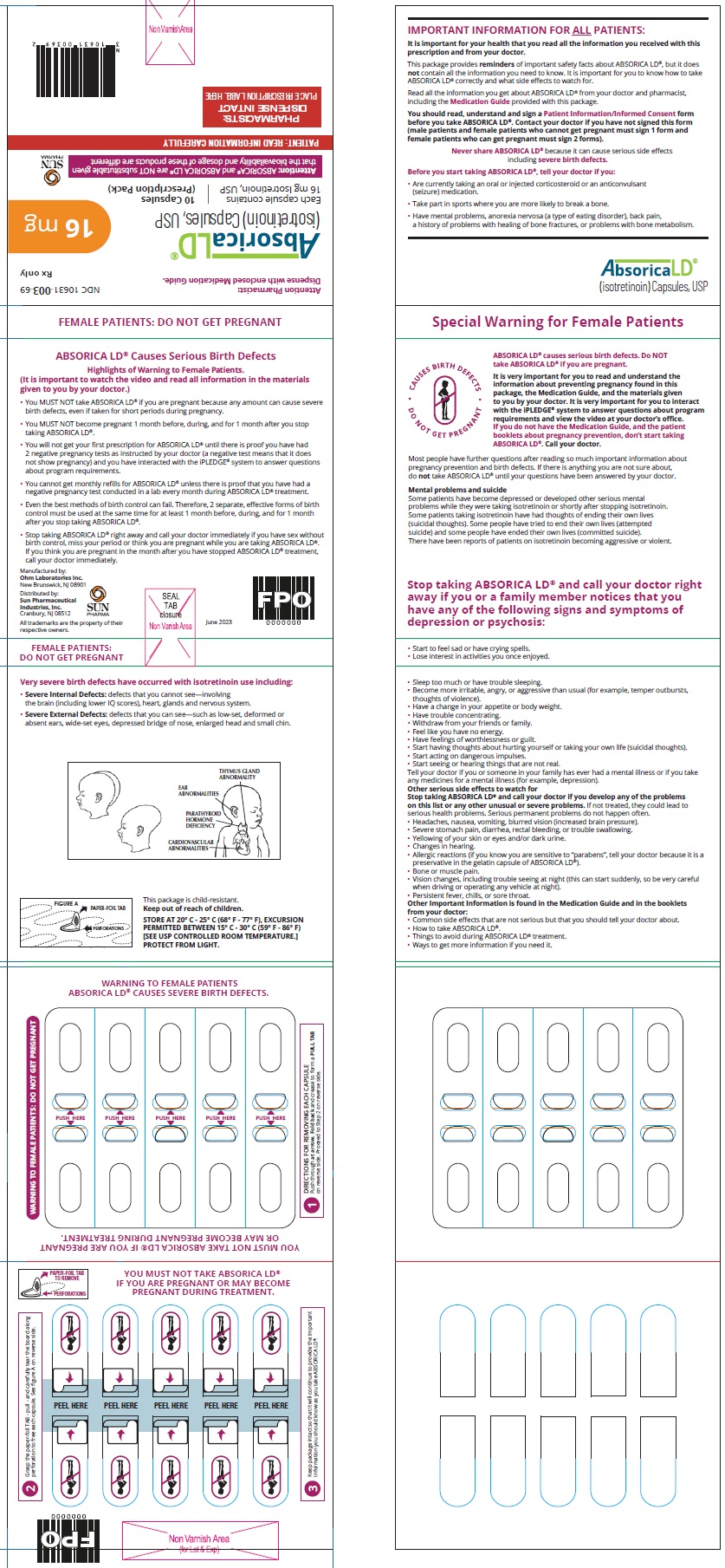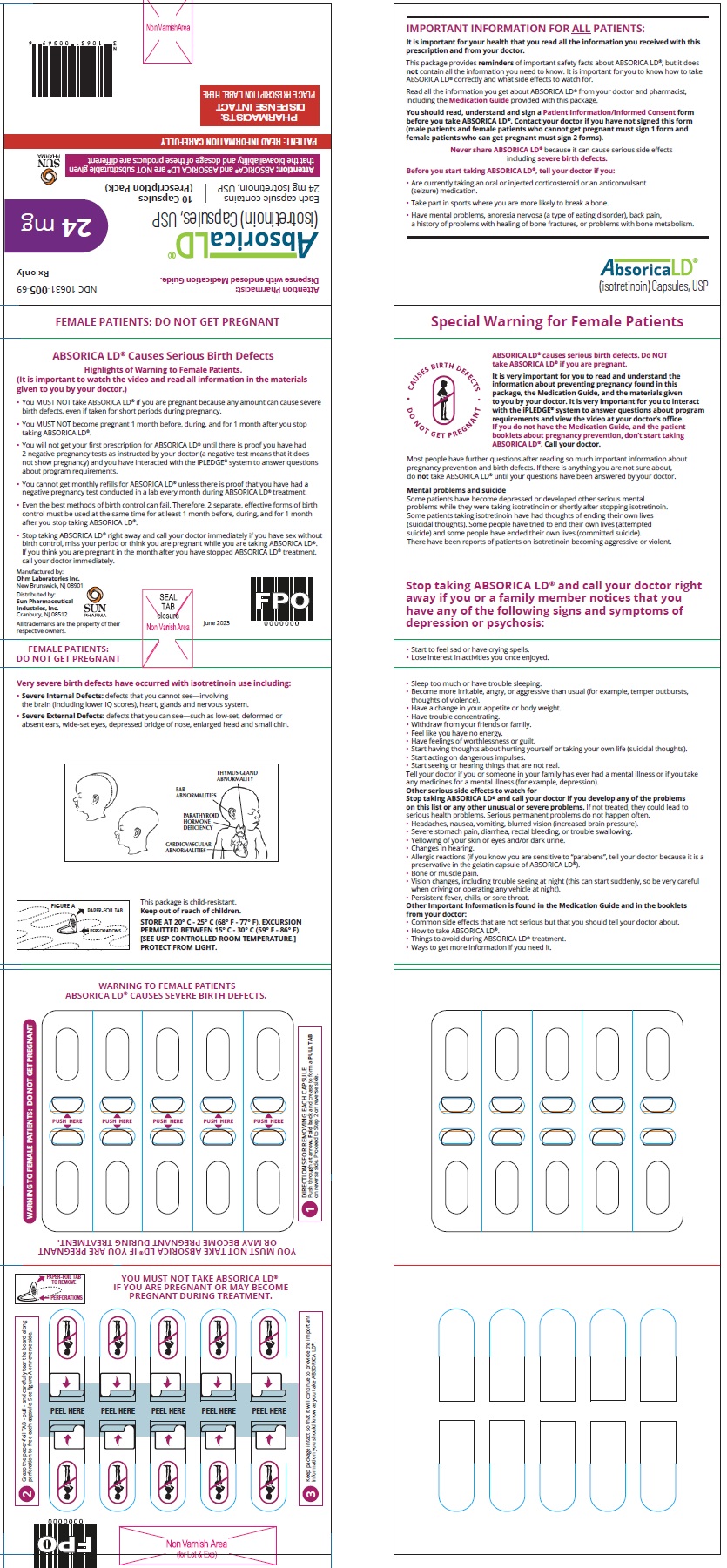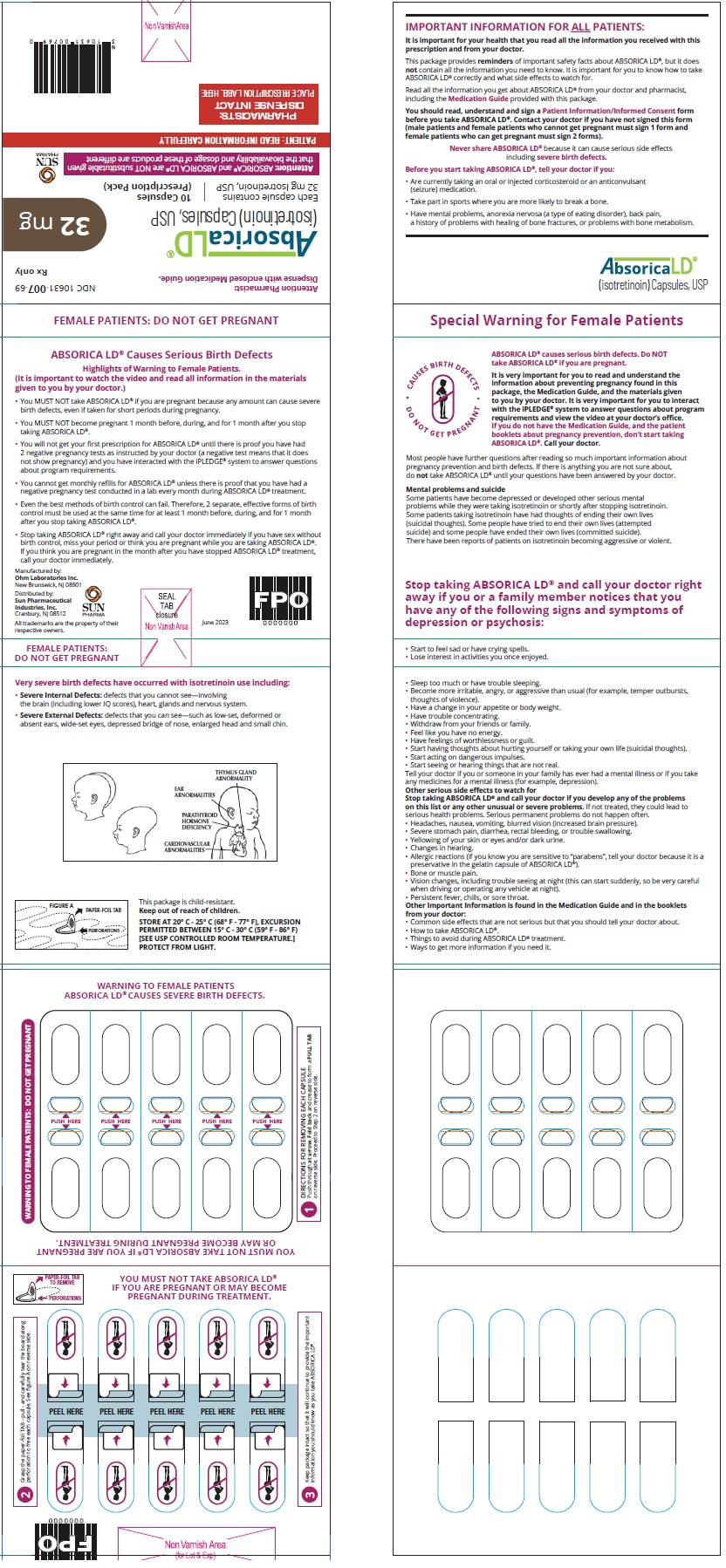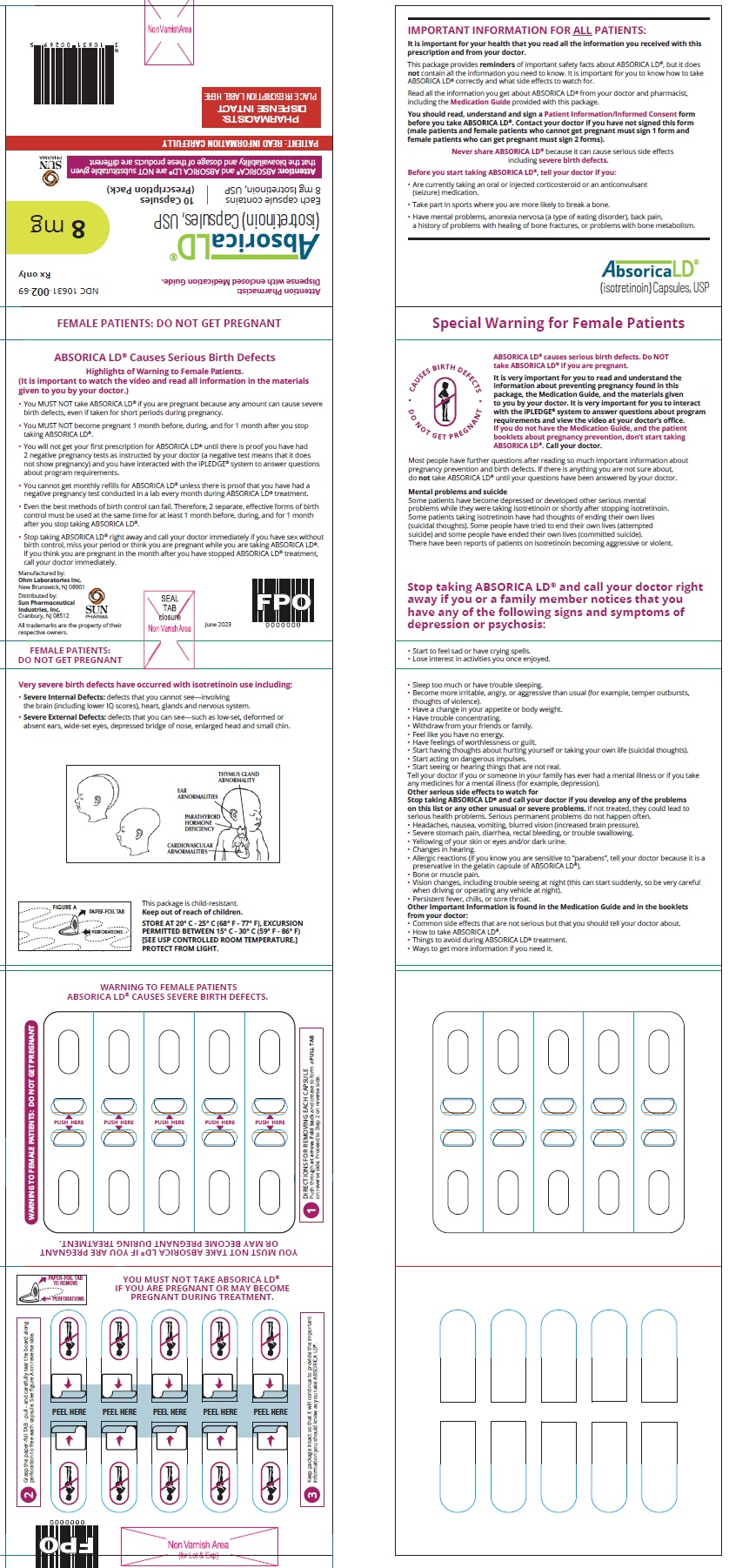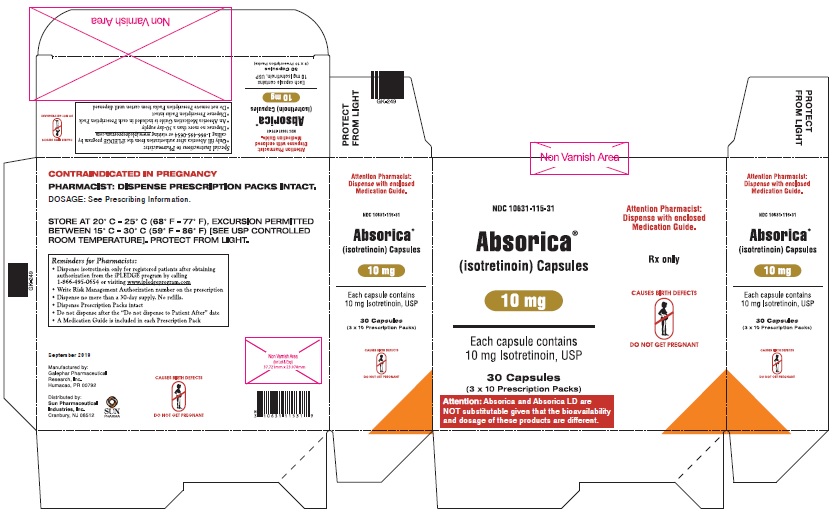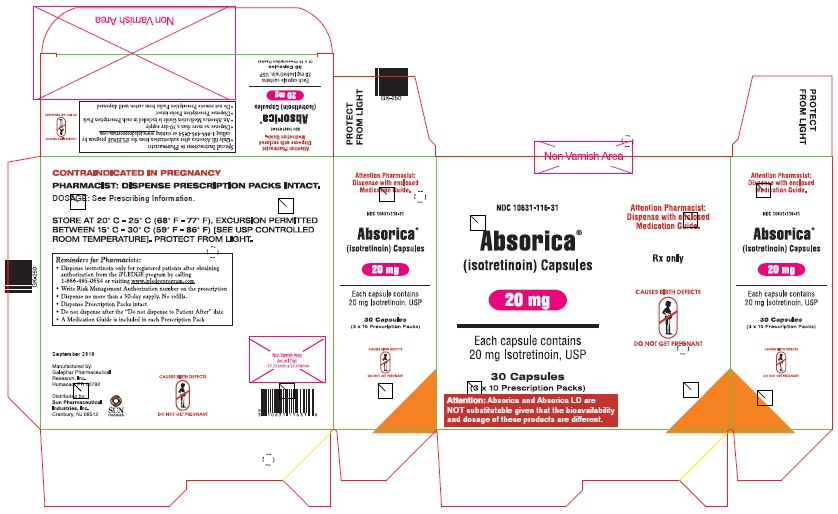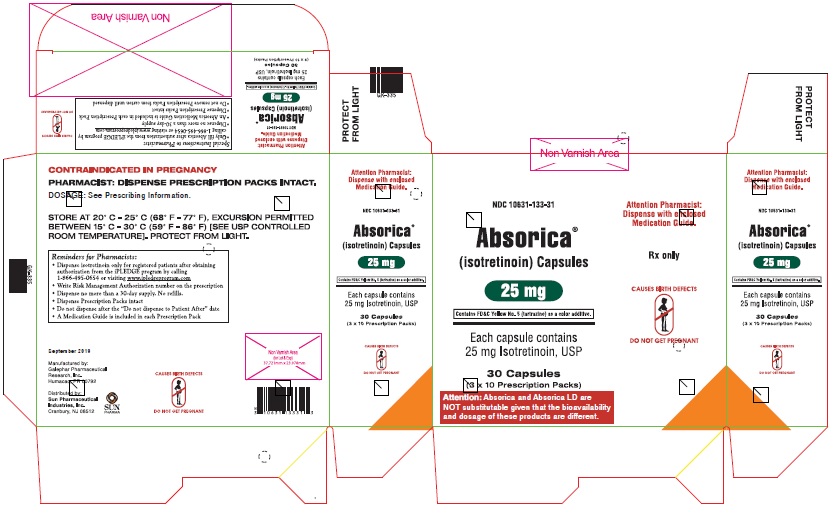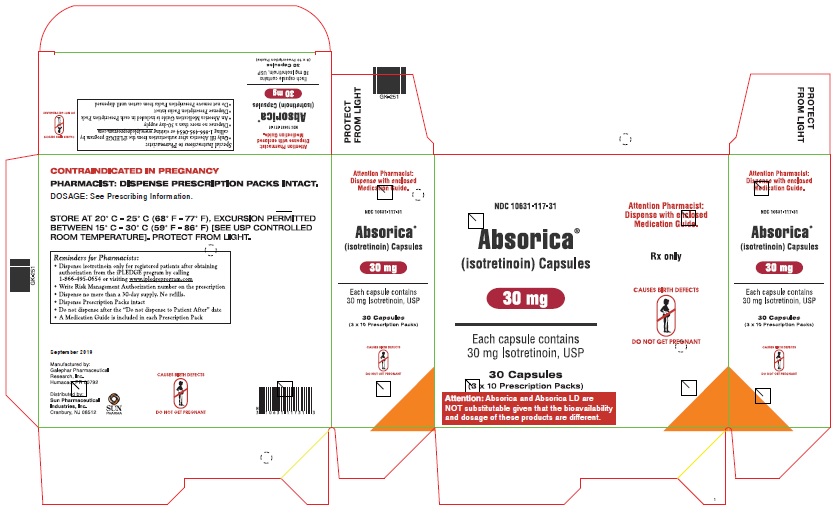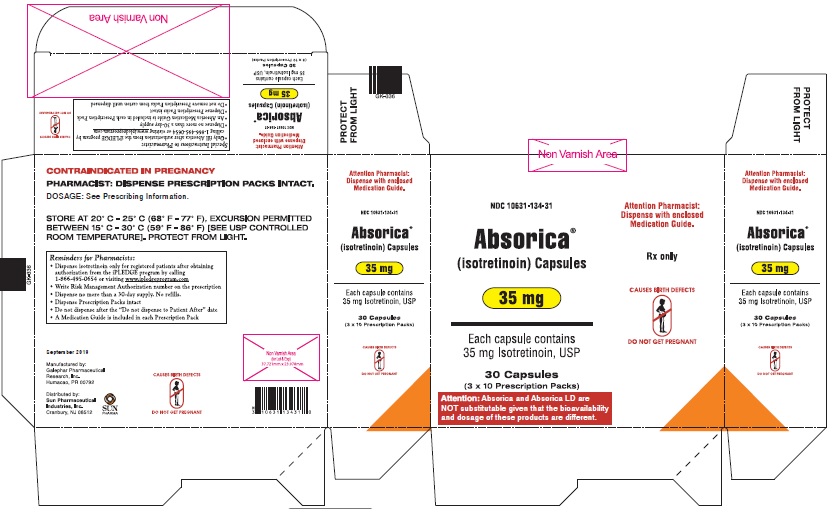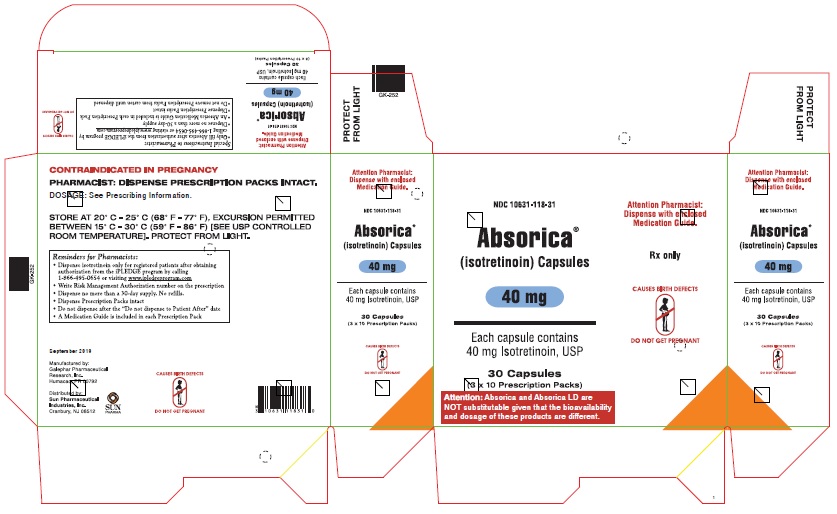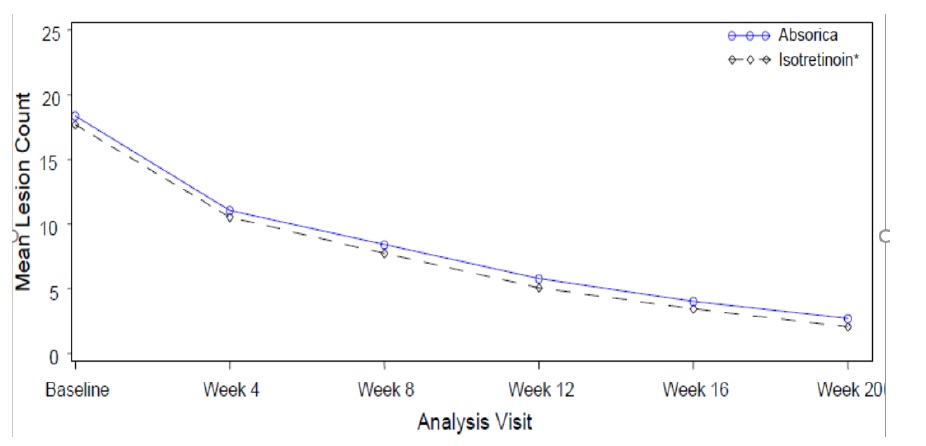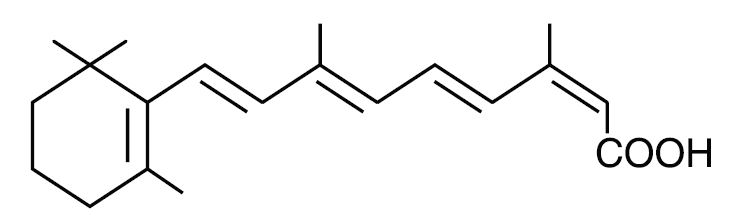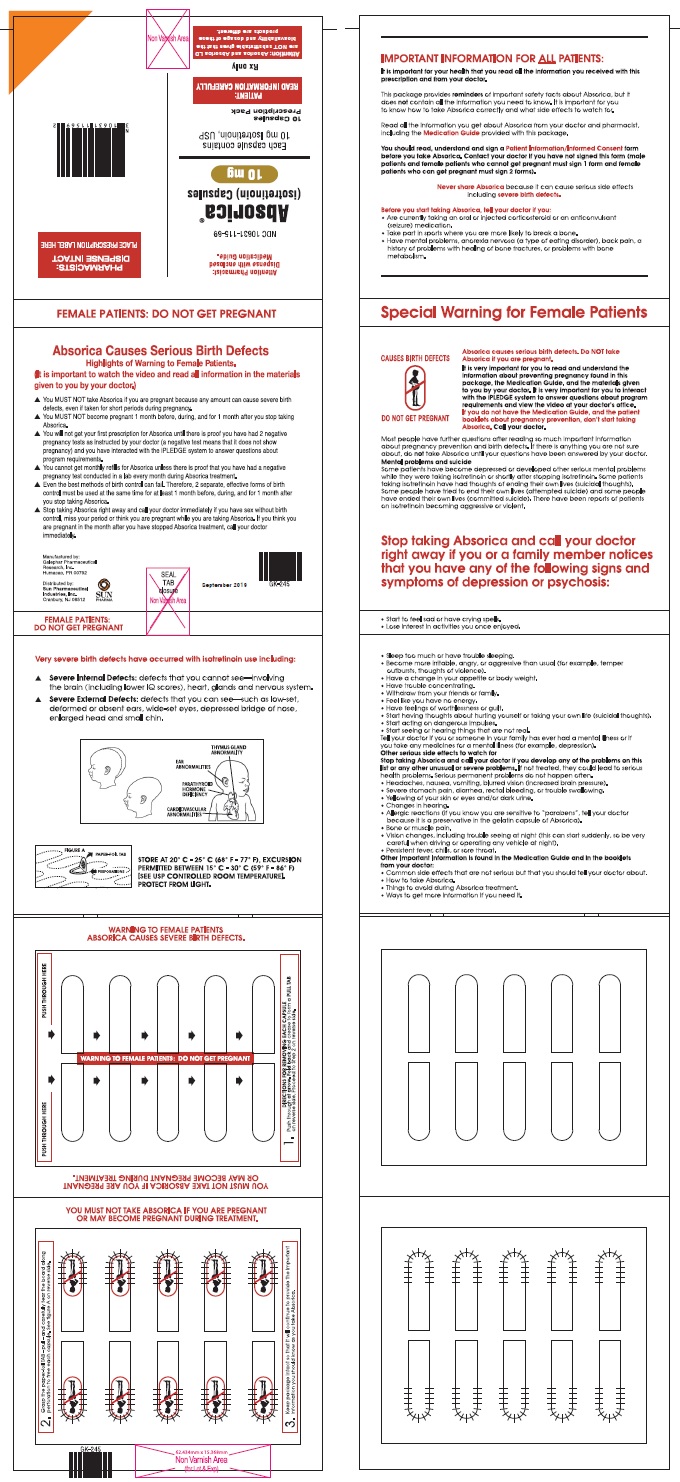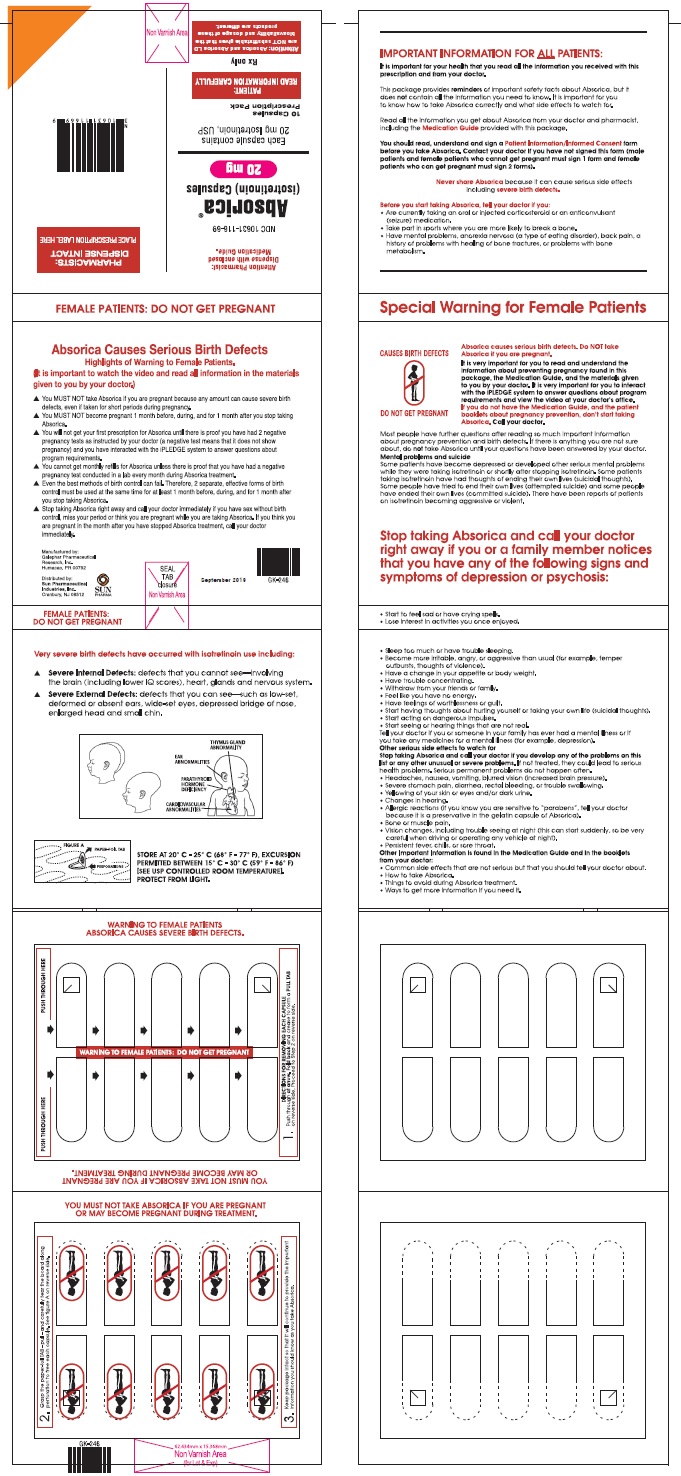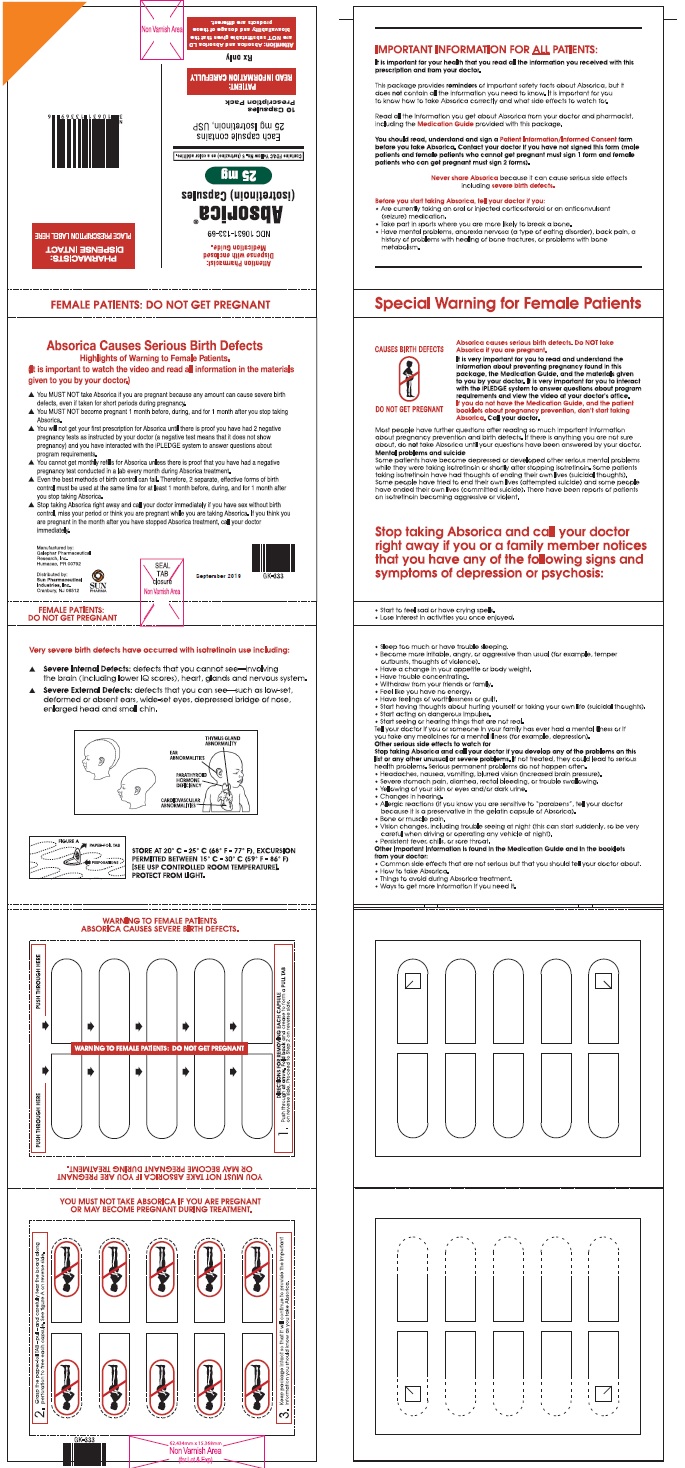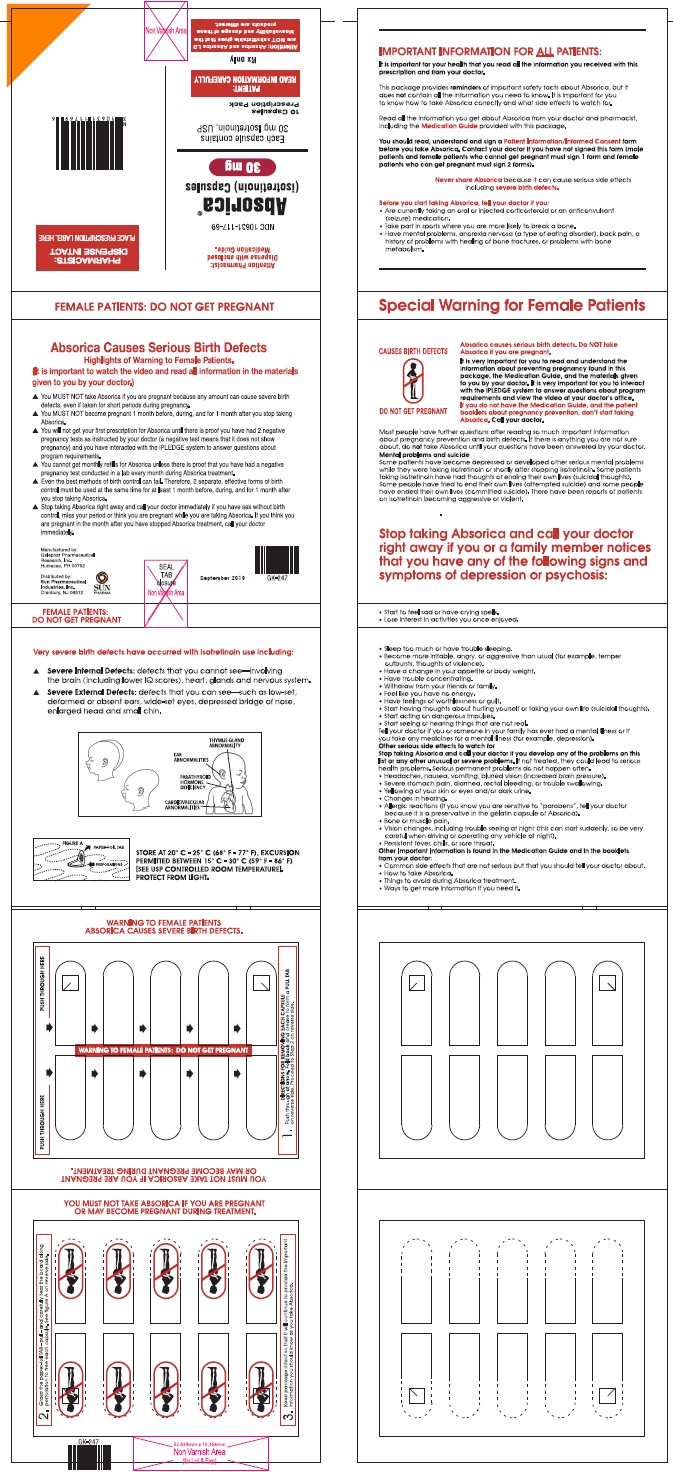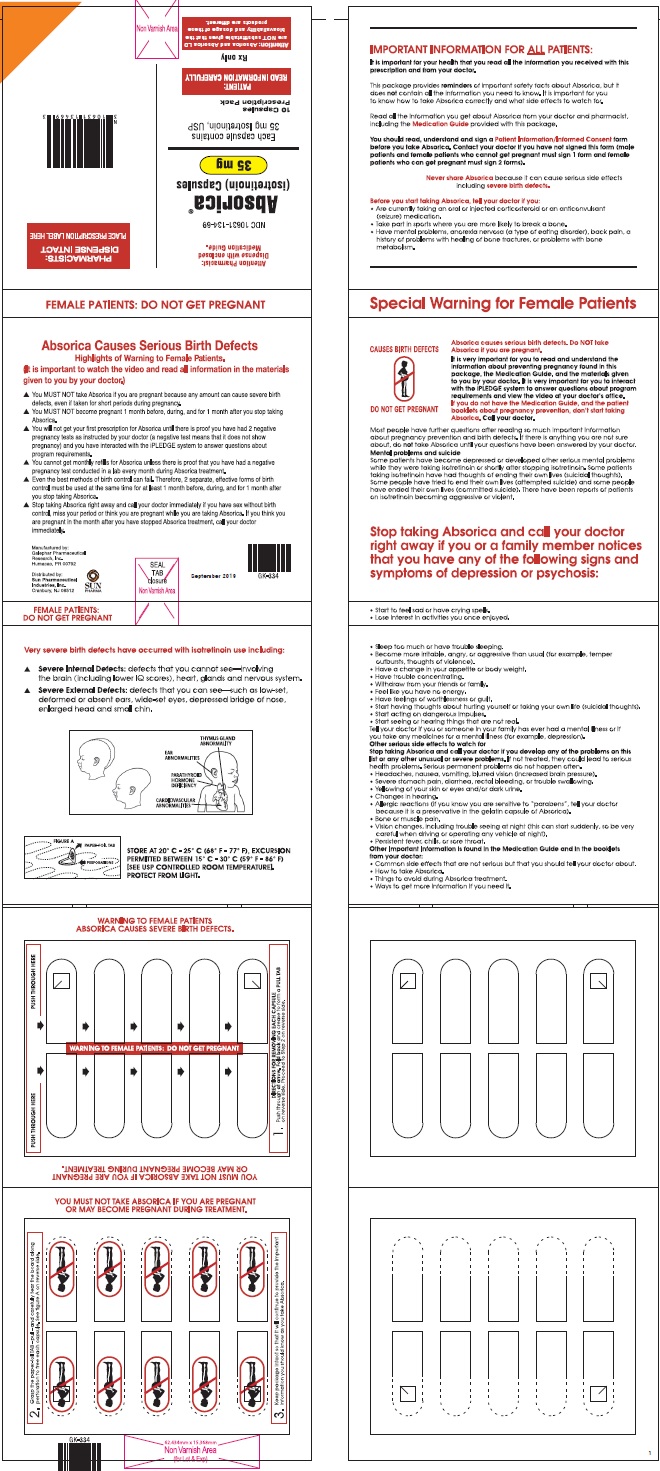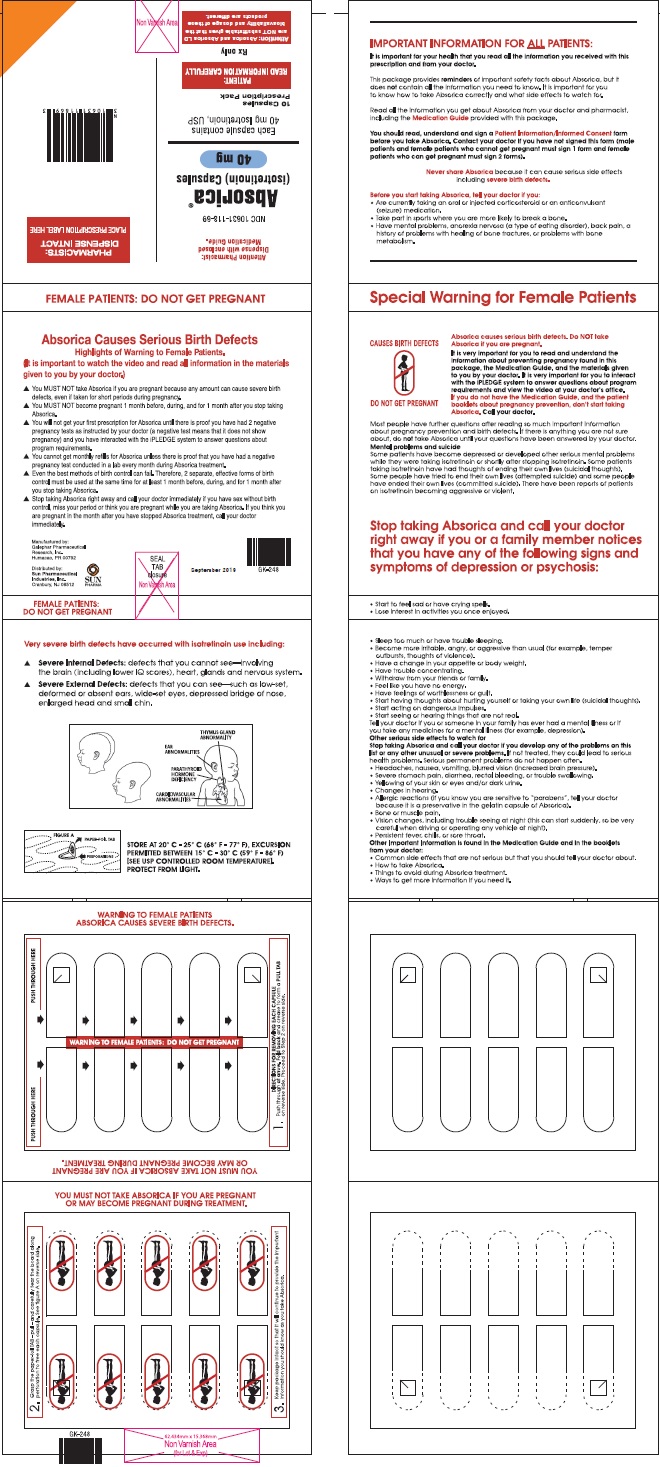 DRUG LABEL: Absorica
NDC: 10631-115 | Form: CAPSULE
Manufacturer: Sun Pharmaceutical Industries, Inc.
Category: prescription | Type: HUMAN PRESCRIPTION DRUG LABEL
Date: 20230612

ACTIVE INGREDIENTS: ISOTRETINOIN 10 mg/1 1
INACTIVE INGREDIENTS: SOYBEAN OIL; SORBITAN MONOOLEATE; PROPYL GALLATE; TITANIUM DIOXIDE; FERRIC OXIDE YELLOW; POTASSIUM HYDROXIDE; PROPYLENE GLYCOL; SHELLAC; PEG-32 HYDROGENATED PALM GLYCERIDES; GELATIN, UNSPECIFIED

HIGHLIGHTS OF PRESCRIBING INFORMATION

These highlights do not include all the information needed to use ABSORICA/ABSORICA LD safely and effectively. See full prescribing information for ABSORICA/ABSORICA LD.
ABSORICA® (isotretinoin) capsules, for oral use
ABSORICA LD® (isotretinoin) capsules, for oral use
Initial U.S. Approval: 1982

WARNING: EMBRYO-FETAL TOXICITY – CONTRAINDICATED IN PREGNANCY

See full prescribing information for complete boxed warning.

- ABSORICA/ABSORICA LD can cause life-threatening birth defects and is contraindicated in pregnancy. There is an extremely high risk that life-threatening birth defects will result if pregnancy occurs while taking ABSORICA/ABSORICA LD in any amount, even for short periods of time. Potentially any fetus exposed during pregnancy can be affected. There are no accurate means of determining whether an exposed fetus has been affected. (4, 5.1, 8.1)
- ABSORICA/ABSORICA LD are available only through a restricted program called the iPLEDGE® REMS. (5.2)

1 INDICATIONS AND USAGE

ABSORICA and ABSORICA LD are retinoids indicated for the treatment of severe recalcitrant nodular acne in non-pregnant patients 12 years of age and older with multiple inflammatory nodules with a diameter of 5 mm or greater. Because of significant adverse reactions associated with its use, ABSORICA and ABSORICA LD are reserved for patients with severe nodular acne who are unresponsive to conventional therapy, including systemic antibiotics. (1)

Limitations of Use:

If a second course of ABSORICA/ABSORICA LD therapy is needed, it is not recommended before a two-month waiting period because the patient’s acne may continue to improve following a 15 to 20-week course of therapy. (1)

2 DOSAGE AND ADMINISTRATION

- ABSORICA is not substitutable with ABSORICA LD because of different bioavailability and recommended dosage. (2.1, 5.3)
- Recommended dosage for:

o ABSORICA is 0.5 to 1 mg/kg/day given in two divided doses without regard to meals for 15 to 20 weeks (2.1)

o ABSORICA LD is 0.4 to 0.8 mg/kg/day given in two divided doses without regard to meals for 15 to 20 weeks (2.1)

- Adult patients with very severe disease (scarring, trunk involvement) may increase dosage to 2 mg/kg/day of ABSORICA (1.6 mg/kg/day of ABSORICA LD) in divided doses. (2.1)
- Once daily dosing is not recommended. (2.1)
- If a dose of ABSORICA/ABSORICA LD is missed, just skip that dose. Do not take two doses of ABSORICA/ABSORICA LD at the same time. (2.1)
- Perform pregnancy tests prior to prescribing, each month during therapy, end of therapy, and one month after discontinuation. (2.3, 8.3)
- Prior to prescribing, perform fasting lipid profile and liver function tests. (2.3)

3 DOSAGE FORMS AND STRENGTHS

ABSORICA Capsules: 10 mg, 20 mg, 25 mg, 30 mg, 35 mg and 40 mg (3)

ABSORICA LD Capsules: 8 mg, 16 mg, 20 mg, 24 mg, 28 mg and 32 mg (3)

4 CONTRAINDICATIONS

- Pregnancy (4.1, 8.1)
- Hypersensitivity to this product or any of its components (4.2, 5.14)

5 WARNINGS AND PRECAUTIONS

- Psychiatric Disorders (depression, psychosis, suicidal thoughts and behavior, and aggressive and/or violent behaviors): Prior to and during therapy assess for these conditions; stop if these conditions occur on therapy (5.4)
- Intracranial Hypertension (Pseudotumor Cerebri): Avoid use with concomitant tetracyclines (5.5)
- Serious Skin Reactions: Monitor for Stevens-Johnson syndrome (SJS), toxic epidermal necrolysis (TEN), and other serious skin reactions (5.6)
- Acute Pancreatitis: If occurs, discontinue treatment (5.7)
- Lipid Abnormalities (hypertriglyceridemia, low HDL, and elevation of cholesterol): Monitor lipid levels at regular intervals; stop if hypertriglyceridemia cannot be controlled (5.8)
- Hearing Impairment: Discontinue and refer to specialized care (5.9)
- Hepatotoxicity: Monitor liver function tests prior to and during therapy (5.10, 5.15)
- Inflammatory Bowel Disease: Discontinue for abdominal pain, rectal bleeding, or severe diarrhea (5.11)
- Musculoskeletal Abnormalities: Arthralgias, back pain, decreases in bone mineral density and premature epiphyseal closure (5.12)
- Ocular Abnormalities e.g., corneal opacities, decreased night vision: If visual symptoms occur, discontinue and refer for an ophthalmological exam (5.13)

6 ADVERSE REACTIONS

Most common adverse reactions (incidence ≥5%) are: dry lips, dry skin, back pain, dry eye, arthralgia, epistaxis, headache, nasopharyngitis, chapped lips, dermatitis, increased creatine kinase, cheilitis, musculoskeletal discomfort, upper respiratory tract infection, reduced visual acuity. (6)

To report SUSPECTED ADVERSE REACTIONS, contact Sun Pharmaceutical Industries, Inc. at 1-800-818-4555 or FDA at 1-800-FDA-1088 or www.fda.gov/medwatch or iPLEDGE at (1-866-495-0654).

7 DRUG INTERACTIONS

- Vitamin A: may cause additive adverse reactions (7.1)
- Tetracyclines: avoid concomitant use (7.2)

8 USE IN SPECIFIC POPULATIONS

Lactation: Breastfeeding not recommended (8.2).

FULL PRESCRIBING INFORMATION

WARNING: EMBRYO-FETAL TOXICITY – CONTRAINDICATED IN PREGNANCY

ABSORICA/ABSORICA LD can cause life-threatening birth defects and is contraindicated in pregnancy.

There is an extremely high risk that life-threatening birth defects will result if pregnancy occurs while taking any amount of ABSORICA/ABSORICA LD even for short periods of time. Potentially any fetus exposed during pregnancy can be affected. There are no accurate means of determining prenatally whether an exposed fetus has been affected. If pregnancy occurs, discontinue ABSORICA/ABSORICA LD immediately and refer the patient to an Obstetrician- Gynecologist experienced in reproductive toxicity for further evaluation and counseling [see Contraindications (4), Warnings and Precautions (5.1), and Use in Specific Populations (8.1)].

Because of the risk of embryo-fetal toxicity, ABSORICA and ABSORICA LD are available only through a restricted program under a Risk Evaluation and Mitigation Strategy (REMS) called the iPLEDGE REMS [see Warnings and Precautions (5.2)].

1 INDICATIONS AND USAGE

ABSORICA and ABSORICA LD are indicated for the treatment of severe recalcitrant nodular acne in non-pregnant patients 12 years of age and older with multiple inflammatory nodules with a diameter of 5 mm or greater. Because of significant adverse reactions associated with its use, ABSORICA and ABSORICA LD are reserved for patients with severe nodular acne who are unresponsive to conventional therapy, including systemic antibiotics.

Limitations of Use:

If a second course of ABSORICA/ABSORICA LD therapy is needed, it is not recommended before a two-month waiting period because the patient’s acne may continue to improve following a 15 to 20-week course of therapy [see Dosage and Administration (2.2)].

2 DOSAGE AND ADMINISTRATION

2.1 Recommended Dosage

ABSORICA is not substitutable with ABSORICA LD [see Warnings and Precautions (5.3)]. The recommended dosage of:

- ABSORICA is 0.5 to 1 mg/kg/day given in two divided doses with or without meals for 15 to 20 weeks (see Table 1).
- ABSORICA LD is 0.4 to 0.8 mg/kg/day given in two divided doses with or without meals for 15 to 20 weeks (see Table 2).

To decrease the risk of esophageal irritation, instruct patients to swallow the capsules with a full glass of liquid. During treatment, the dosage may be adjusted according to response of the disease and/or adverse reactions, some of which may be dose-related. Adult patients whose disease is very severe with scarring or is primarily manifested on the trunk may require dosage adjustments up to 2 mg/kg/day for ABSORICA (1.6 mg/kg/day for ABSORICA LD) in divided doses, as tolerated.

The safety and effectiveness of once daily dosing with ABSORICA/ABSORICA LD has not been established and is not recommended.

If a dose of ABSORICA/ABSORICA LD is missed, just skip that dose. Do not take two doses of ABSORICA/ ABSORICA LD at the same time.

Table 1: ABSORICA Daily Dosage by Body Weight^1
Body; Weight | Total Daily Dosage (mg)^1
Body; Weight | 0.5 mg/kg | 1 mg/kg | 2 mg/kg
40 kg | 20 | 40 | 80
50 kg | 25 | 50 | 100
60 kg | 30 | 60 | 120
70 kg | 35 | 70 | 140
80 kg | 40 | 80 | 160
90 kg | 45 | 90 | 180
100 kg | 50 | 100 | 200

^1 Administer in two divided doses with or without meals

Table 2: ABSORICA LD Daily Dosage by Body Weight^1

Body; Weight | Total Daily Dosage (mg)^1
Body; Weight | 0.4 mg/kg | 0.8 mg/kg | 1.6 mg/kg
40 kg | 16 | 32 | 64
50 kg | 20 | 40 | 80
60 kg | 24 | 48 | 96
70 kg | 28 | 56 | 112
80 kg | 32 | 64 | 128
90 kg | 36 | 72 | 144
100 kg | 40 | 80 | 160

^1 Administer in two divided doses with or without meals

2.2 Duration of Use

A normal course of treatment is 15 to 20 weeks. If the total nodule count has been reduced by more than 70% prior to completing 15 to 20 weeks of treatment, may discontinue ABSORICA/ABSORICA LD.

After a period of 2 months or more off therapy, and if warranted by persistent or recurring severe nodular acne, may initiate a second course of ABSORICA/ABSORICA LD in patients who have completed skeletal growth. The use of another course of ABSORICA/ABSORICA LD therapy is not recommended before a two-month waiting period because the patient’s acne may continue to improve after a 15 to 20-week course of therapy. The optimal interval before retreatment has not been defined for patients who have not completed skeletal growth.

Long-term use of ABSORICA/ABSORICA LD, even in low dosages, has not been studied, and is not recommended. The effect of long-term use of ABSORICA/ABSORICA LD on bone loss is unknown [see Warnings and Precautions (5.12)].

2.3 Laboratory Testing Prior to Administration

The following laboratory testing must be completed prior to ABSORICA/ABSORICA LD use:

- Pregnancy testing: Ensure patient is not pregnant prior to administering ABSORICA/ABSORICA LD [see Contraindications (4) and Use in Specific Populations (8.1, 8.3)]
- A fasting lipid profile including triglycerides [see Warnings and Precautions (5.8, 5.15)].
- Liver function tests [see Warnings and Precautions (5.10, 5.15)].

3 DOSAGE FORMS AND STRENGTHS

ABSORICA and ABSORICA LD have different dosage regimens [see Dosage and Administration (2.1)]. Although ABSORICA and ABSORICA LD have a 20 mg strength, these strengths have different bioavailability and are not substitutable.

ABSORICA is available in 10 mg, 20 mg, 25 mg, 30 mg, 35 mg and 40 mg capsules.

- 10 mg: Dark yellow, opaque, capsule imprinted with black ink “G 240” on cap and “10” on the body
- 20 mg: Red, opaque, capsule imprinted with black ink “G 241” on cap and “20” on the body
- 25 mg: Green, opaque, capsule imprinted with white ink “G 342” on cap and “25” on the body
- 30 mg: Brown, opaque, capsule imprinted with white ink “G 242” on cap and “30” on the body
- 35 mg: Dark blue, opaque, capsule imprinted with white ink “G 343” on cap and “35” on the body
- 40 mg: Brown and red, capsule imprinted with white ink “G 325” on cap and “40” on the body

ABSORICA LD is available in 8 mg, 16 mg, 20 mg, 24 mg, 28 mg and 32 mg opaque-printed, hard-gelatin capsules.

- 8 mg: A size 3, light green with a colorless band (the cap is printed in white with “RL29” and the body is printed in white with “RL29”).
- 16 mg: A size 2, dark blue with a colorless band (the cap is printed in white with “RL30” and the body is printed in white with “RL30”).
- 20 mg: A size 1, dark pink with a colorless band (the cap is printed in black with “RL33”and the body is printed in black with “RL33”).
- 24 mg: A size 1, yellow with a colorless band (the cap is printed in white with “RL31” and the body is printed in white with “RL31”).
- 28 mg: A size 0, light blue, with a colorless band (the cap is printed in black with “RL34” and the body is printed in black with “RL34”).
- 32 mg: A size 0, caramel with a colorless band (the cap is printed in white with “RL32” and the body is printed in white with “RL32”).

4 CONTRAINDICATIONS

4.1 Pregnancy

ABSORICA/ABSORICA LD is contraindicated in pregnancy [see Warnings and Precautions (5.1) and Use in Specific Populations (8.1)].

4.2 Hypersensitivity

ABSORICA/ABSORICA LD is contraindicated in patients with hypersensitivity to isotretinoin (or Vitamin A, given the chemical similarity to isotretinoin) or to any of its components (anaphylaxis and other allergic reactions have occurred) [see Warnings and Precautions (5.14)].

5 WARNINGS AND PRECAUTIONS

5.1 Embryo-Fetal Toxicity

ABSORICA/ABSORICA LD is contraindicated in pregnancy [see Contraindications (4.1)]. Based on human data, ABSORICA/ABSORICA LD can cause fetal harm when administered to a pregnant patient. There is an extremely high risk that life-threatening birth defects will result if pregnancy occurs while taking any amount of ABSORICA/ABSORICA LD even for short periods of time. Potentially any fetus exposed during pregnancy can be affected. There are no accurate means of determining prenatally whether an exposed fetus has been affected. Major congenital malformations, spontaneous abortions, and premature births have been documented following exposure to isotretinoin during pregnancy [see Use in Specific Populations (8.1)].

If a pregnancy occurs during ABSORICA/ABSORICA LD treatment, discontinue ABSORICA/ABSORICA LD immediately and refer the patient to an obstetrician/gynecologist experienced in reproductive toxicity for further evaluation and counseling. Any suspected fetal exposure during or 1 month after ABSORICA/ABSORICA LD therapy must be reported immediately to the FDA via the MedWatch telephone number 1-800-FDA-1088, and also to the iPLEDGE pregnancy registry at 1-866-495-0654 or via the internet (www.ipledgeprogram.com).

Patients must be informed not to donate blood during ABSORICA/ABSORICA LD therapy and for 1 month following discontinuation because the blood might be given to a pregnant patient whose fetus must not be exposed to isotretinoin.

ABSORICA/ABSORICA LD is available only through a restricted program under a REMS [see Warnings and Precautions (5.2)].

5.2 iPLEDGE Program

ABSORICA/ABSORICA LD are available only through a restricted program under a REMS called the iPLEDGE REMS because of the risk of embryo-fetal toxicity [see Warnings and Precautions (5.1)]. Notable requirements of the iPLEDGE REMS include the following:

- Prescribers must be certified with the program and comply with the following requirements:
  Determine reproductive status of all patients prior to initiating treatment
- Provide contraception counseling to patients who can get pregnant prior to and during treatment, or refer patients who can get pregnant to an expert for such counseling
- Provide scheduled pregnancy testing, and verify and document the negative pregnancy test result prior to writing each prescription, for no more than a 30-day supply
- Patients who can become pregnant must be enrolled by signing an informed consent form and must comply with the following requirements
- Comply with the pregnancy testing and contraception requirements [see Use in Specific Populations (8.3)]
- Demonstrate comprehension of the safe-use conditions of the program every month
- Obtain the prescription within 7 days of the pregnancy test collection
- Patients who cannot become pregnant must be enrolled by signing an informed consent form and must obtain the prescription within 30 days of the office visit
- Pharmacies that dispense ABSORICA/ABSORICA LD must be certified by being registered and activated in the program, must only dispense to patients who are authorized to receive ABSORICA/ABSORICA LD, and comply with the following requirements:
  o Only dispense a maximum of a 30-day supply with a Medication Guide.
  o Do not dispense refills. Dispense only with a new prescription and a new authorization from the program.
  o Return ABSORICA/ABSORICA LD to inventory if patients do not obtain the prescription by the “Do Not Dispense To After” date
- Wholesalers and distributors must be registered with the program and must only distribute to certified pharmacies.

Further information, including a list of qualified pharmacies and distributors, is available at www.ipledgeprogram.com or 1-866-495-0654.

5.3 ABSORICA and ABSORICA LD are Not Substitutable

Given that the bioavailability and the recommended dosage of ABSORICA and ABSORICA LD are different, ABSORICA and ABSORICA LD are not substitutable. For example, ABSORICA and ABSORICA LD have a 20 mg strength; however, these strengths have different bioavailability and are not substitutable.

5.4 Psychiatric Disorders

ABSORICA/ABSORICA LD may cause depression, psychosis and, rarely, suicidal ideation, suicide attempts, suicide, and aggressive and/or violent behaviors [see Adverse Reactions (6)].

Healthcare providers should be alert to the warning signs of psychiatric disorders to help ensure patients receive the help they need (Prescribers should read the brochure, Recognizing Psychiatric Disorders in Adolescents and Young Adults: A Guide for Prescribers of Isotretinoin). Prior to initiation of ABSORICA/ABSORICA LD therapy, patients and family members should be asked about any history of psychiatric disorder, and at each visit during therapy patients should be assessed for symptoms of depression, mood disturbance, psychosis, or aggression to determine if further evaluation is necessary.

Patients should immediately stop ABSORICA/ABSORICA LD and the patient (or caregiver) should promptly contact their prescriber if the patient develops depression, mood disturbance, psychosis, or aggression. Discontinuation of ABSORICA/ABSORICA LD may be insufficient; further evaluation may be necessary such as a referral to a mental healthcare professional.

5.5 Intracranial Hypertension (Pseudotumor Cerebri)

Isotretinoin use has been associated with cases of intracranial hypertension (pseudotumor cerebri), some of which involved concomitant use of tetracyclines. Concomitant treatment with tetracyclines should therefore be avoided with ABSORICA/ABSORICA LD use. Early signs and symptoms of intracranial hypertension include papilledema, headache, nausea and vomiting, and visual disturbances. Patients with these symptoms should be screened for papilledema and, if present, they should be told to discontinue ABSORICA/ABSORICA LD immediately and be referred to a neurologist for further diagnosis and care [see Adverse Reactions (6)].

5.6 Serious Skin Reactions

There have been postmarketing reports of erythema multiforme and severe skin reactions [e.g., Stevens-Johnson syndrome (SJS), toxic epidermal necrolysis (TEN)] associated with isotretinoin use. These reactions may be serious and result in death, life-threatening events, hospitalization, or disability. Patients should be monitored closely for severe skin reactions, and ABSORICA/ABSORICA LD should be discontinued if they occur.

5.7 Pancreatitis

Acute pancreatitis has been reported with isotretinoin use in patients with either elevated or normal serum triglyceride levels. In rare instances, fatal hemorrhagic pancreatitis has been reported. If symptoms of pancreatitis occur, discontinue ABSORICA/ABSORICA LD and seek medical attention.

5.8 Lipid Abnormalities

Elevations of serum triglycerides above 800 mg/dL have been reported with isotretinoin use. In clinical trials, marked elevations of serum triglycerides, decreases in high-density lipoproteins (HDL), and increases in cholesterol levels were reported in 25%, 15%, and 7% of patients treated with isotretinoin capsules, respectively. These lipid changes were reversible upon isotretinoin capsule cessation. Some patients have been able to reverse triglyceride elevation by reduction in weight and restriction of dietary fat and alcohol while continuing isotretinoin or through dosage reduction. The cardiovascular consequences of hypertriglyceridemia associated with isotretinoin are unknown.

Fasting lipid tests should be performed before ABSORICA/ABSORICA LD treatment and then at intervals until the lipid response to ABSORICA/ABSORICA LD is known, which usually occurs within 4 weeks. Careful consideration should be given to risk/benefit of ABSORICA/ABSORICA LD in patients who are at higher risk of hypertriglyceridemia (e.g., patients with diabetes, obesity, increased alcohol intake, lipid metabolism disorder or familial history of lipid metabolism disorder). If ABSORICA/ABSORICA LD therapy is instituted in such patients, more frequent checks of serum values for lipids are recommended [see Warnings and Precautions (5.15)]. ABSORICA/ABSORICA LD should be stopped if hypertriglyceridemia cannot be controlled.

5.9 Hearing Impairment

Impaired hearing has been reported in patients taking isotretinoin; in some cases, the hearing impairment has been reported to persist after therapy has been discontinued. Mechanism(s) and causality for this reaction have not been established. Patients who experience tinnitus or hearing impairment should discontinue ABSORICA/ABSORICA LD treatment and be referred for specialized care for further evaluation.

5.10 Hepatotoxicity

Clinical hepatitis has been reported with isotretinoin use. Additionally, mild to moderate elevations of liver enzymes have been observed in approximately 15% of individuals treated during clinical trials with isotretinoin capsules, some of which normalized with dosage reduction or continued administration of the drug. If normalization does not readily occur or if hepatitis is suspected during treatment, ABSORICA/ABSORICA LD should be discontinued.

5.11 Inflammatory Bowel Disease

Isotretinoin has been associated with inflammatory bowel disease (including regional ileitis) in patients without a prior history of intestinal disorders. In some instances, symptoms have been reported to persist after isotretinoin treatment has been stopped. Patients experiencing abdominal pain, rectal bleeding or severe diarrhea should discontinue ABSORICA/ABSORICA LD immediately [see Adverse Reactions (6)].

5.12 Musculoskeletal Abnormalities

Bone Mineral Density Changes, Osteoporosis, and Fractures

Isotretinoin may have a negative effect on bone mineral density (BMD) in some patients. In a clinical trial of ABSORICA and another isotretinoin capsule product, 27/306 (9%) of adolescents had BMD declines, defined as ≥ 4% lumbar spine or total hip, or ≥ 5% femoral neck, during the 20-week treatment period. Repeat scans conducted within 2 to 3 months after the post-treatment scan showed no recovery of BMD. Long-term data at 4 to 11 months showed that 3 out of 7 patients had total hip and femoral neck BMD below pre-treatment baseline, and 2 others did not show the increase in BMD above baseline expected in this adolescent population. Therefore, healthcare providers should use caution when prescribing ABSORICA/ABSORICA LD to patients with a history of childhood osteoporosis conditions, osteomalacia, or other disorders of bone metabolism. This would include patients diagnosed with anorexia nervosa and those who are on chronic drug therapy that causes drug-induced osteoporosis/osteomalacia and/or affects vitamin D metabolism, such as systemic corticosteroids and any anticonvulsant [see Use in Specific Populations (8.4)].

There have been spontaneous reports of osteoporosis, osteopenia, fractures and/or delayed healing of fractures in patients while on therapy with isotretinoin or following cessation of therapy with isotretinoin.

Patients in early and late adolescence who participate in sports with repetitive impact may be at an increased risk of spondylolisthesis with and without pars fractures, and hip growth plate injuries have been reported.

Musculoskeletal Abnormalities

Approximately 16% of patients treated with isotretinoin capsules in a clinical trial developed musculoskeletal symptoms (including arthralgia) during treatment. In general, these symptoms were mild to moderate, but occasionally required discontinuation of isotretinoin.

In a trial of pediatric patients treated with isotretinoin capsules, approximately 29% (104/358) developed back pain. Back pain was severe in 14% (14/104) of the cases and occurred at a higher frequency in female patients than male patients.

Arthralgias were experienced in 22% (79/358) of pediatric patients. Arthralgias were severe in 8% (6/79) of patients. Appropriate evaluation of the musculoskeletal system should be done in patients who present with these symptoms during or after a course of ABSORICA/ABSORICA LD. Consider discontinuing ABSORICA/ABSORICA LD if any significant abnormality is found.

Effects of multiple courses of isotretinoin on the developing musculoskeletal system are unknown. There is some evidence that long-term, high-dose, or multiple courses of therapy with isotretinoin have more of an effect than a single course of therapy on the musculoskeletal system. It is important that ABSORICA/ABSORICA LD be given at the recommended dose for no longer than the recommended duration.

Hyperostosis

A high prevalence of skeletal hyperostosis was noted in clinical trials for disorders of keratinization with a mean dose of 2.24 mg/kg/day of isotretinoin capsules (approximately 1.1 times the maximum recommended daily dosage). Additionally, skeletal hyperostosis was noted in 6 of 8 patients in a prospective trial of disorders of keratinization. Minimal skeletal hyperostosis and calcification of ligaments and tendons have also been observed by x-ray in prospective trials of nodular acne patients treated with a single course of therapy at recommended doses. The skeletal effects of multiple isotretinoin treatment courses for acne are unknown.

In a clinical trial of 217 pediatric patients (12 to 17 years) with severe recalcitrant nodular acne, hyperostosis was not observed after 16 to 20 weeks of treatment with approximately 1 mg/kg/day of isotretinoin capsules given in two divided doses. Hyperostosis may require a longer time frame to appear. The clinical course and significance remain unknown.

Premature Epiphyseal Closure

There are spontaneous literature reports of premature epiphyseal closure in acne patients receiving recommended doses of isotretinoin capsules. The effect of multiple courses of isotretinoin on epiphyseal closure is unknown.

In a 20-week clinical trial that included 289 adolescents on ABSORICA or another isotretinoin capsule product who had hand radiographs taken to assess bone age, a total of 9 (3%) patients had bone age changes that were clinically significant and for which a drug-related effect cannot be excluded.

5.13 Ocular Abnormalities

Visual problems should be carefully monitored. If visual difficulties occur, discontinue ABSORICA/ABSORICA LD treatment and obtain an ophthalmological examination [see Adverse Reactions (6)].

Corneal Opacities

Corneal opacities have occurred in patients receiving isotretinoin capsules and more frequently when higher drug dosages were used in patients with disorders of keratinization. The corneal opacities that have been observed in clinical trial patients treated with isotretinoin capsules have either completely resolved or were resolving at follow-up 6 to 7 weeks after discontinuation of isotretinoin [see Adverse Reactions (6)].

Decreased Night Vision

Decreased night vision has been reported during isotretinoin use and in some instances the event has persisted after therapy was discontinued. Because the onset in some patients was sudden, patients should be advised of this potential problem and warned to be cautious when driving or operating any vehicle at night.

Dry Eyes

Dry eyes has been reported in patients during isotretinoin use. Patients who wear contact lenses may have trouble wearing them while on ABSORICA/ABSORICA LD treatment and afterwards.

5.14 Hypersensitivity Reactions

Anaphylactic reactions and other allergic reactions have been reported with isotretinoin use. Cutaneous allergic reactions and serious cases of allergic vasculitis, often with purpura (bruises and red patches) of the extremities and extracutaneous involvement (including renal) have been reported. Severe allergic reaction necessitates discontinuation of therapy and appropriate medical management.

Allergic Reactions Due to the Inactive Ingredient (FD&C Yellow No. 5) in the 25 mg ABSORICA Capsule

The 25 mg ABSORICA capsule contains FD&C Yellow No. 5 (tartrazine) which may cause allergic-type reactions (including bronchial asthma) in certain susceptible persons. Although the overall incidence of tartrazine sensitivity in the general population is low, it is frequently seen in patients who also have aspirin hypersensitivity. The 10 mg, 20 mg, 30 mg, 35 mg, and 40 mg ABSORICA capsules do not contain FD&C Yellow No. 5 and all of the ABSORICA LD capsules do not contain FD&C Yellow No. 5. Thus, in patients with allergic reactions to tartrazine, avoid using the 25 mg ABSORICA capsules.

5.15 Laboratory Abnormalities and Laboratory Monitoring for Adverse Reactions

Laboratory Monitoring

Pregnancy Testing

A pregnancy test must be obtained prior to obtaining a prescription, repeated each month, at the end of the entire course of ABSORICA/ABSORICA LD therapy and 1 month after the discontinuation of ABSORICA/ABSORICA LD [see Use in Specific Populations (8.3)].

Lipid Tests

Pretreatment and follow-up fasting lipid tests should be obtained under fasting conditions. After consumption of alcohol, at least 36 hours should elapse before testing is performed. It is recommended that these tests be performed periodically until the lipid response to ABSORICA/ABSORICA LD is known. The incidence of hypertriglyceridemia is 25% in patients treated with isotretinoin capsules [see Warnings and Precautions (5.8)].

Liver Function Tests

As elevations of liver enzymes have been observed during clinical trials, and hepatitis has been reported in patients on isotretinoin capsules, pretreatment and follow-up liver function tests should be performed periodically until the response to ABSORICA/ABSORICA LD is known [see Warnings and Precautions (5.10)].

Additional Laboratory Abnormalities

Glucose

With isotretinoin use, some patients have experienced problems in the control of their blood sugar. In addition, new cases of diabetes have been diagnosed during isotretinoin use.

CPK

Some patients undergoing vigorous physical activity while taking isotretinoin have experienced elevated CPK levels; however, the clinical significance is unknown. There have been rare postmarketing reports of rhabdomyolysis with isotretinoin use, some associated with strenuous physical activity. In a clinical trial of 924 patients, marked elevations in CPK (≥350 U/L) were observed in approximately 24% of patients treated with isotretinoin capsules.

In another clinical trial of 217 pediatric patients (12 to 17 years old) elevations in CPK were observed in 12% of patients, including those undergoing strenuous physical activity in association with reported musculoskeletal adverse events such as back pain, arthralgia, limb injury, or muscle sprain. In these patients, approximately half of the CPK elevations returned to normal within 2 weeks and half returned to normal within 4 weeks. No cases of rhabdomyolysis were reported in this clinical trial.

6 ADVERSE REACTIONS

The following adverse reactions with ABSORICA/ABSORICA LD or other isotretinoin capsule products are described in more detail in other sections of the labeling:

- Embryo-Fetal Toxicity [see Warnings and Precautions (5.1)]
- Psychiatric Disorders [see Warnings and Precautions (5.4)]
- Intracranial Hypertension (Pseudotumor Cerebri) [see Warnings and Precautions (5.5)]
- Serious Skin Reactions [see Warnings and Precautions (5.6)]
- Pancreatitis [see Warnings and Precautions (5.7)]
- Lipid Abnormalities [see Warnings and Precautions (5.8)]
- Hearing Impairment [see Warnings and Precautions (5.9)]
- Hepatotoxicity [see Warnings and Precautions (5.10)]
- Inflammatory Bowel Disease [see Warnings and Precautions (5.11)]
- Musculoskeletal Abnormalities [see Warnings and Precautions (5.12)]
- Ocular Abnormalities [see Warnings and Precautions (5.13)]
- Hypersensitivity Reactions [see Warnings and Precautions (5.14)]

The following adverse reactions associated with the use of isotretinoin capsules were identified in clinical studies or postmarketing reports. Because some of these reactions were reported voluntarily from a population of uncertain size, it is not always possible to reliably estimate their frequency or establish a causal relationship to drug exposure.

Dose Relationship

Cheilitis and hypertriglyceridemia were dose related.

Body as a Whole

Fatigue, irritability, pain, allergic reactions, systemic hypersensitivity, edema, lymphadenopathy, weight loss.

Cardiovascular

Vascular thrombotic disease, stroke, palpitation, tachycardia.

Endocrine/Metabolism and Nutritional

Decreased appetite, weight fluctuation, alterations in blood sugar.

Gastrointestinal

Dry lips, chapped lips, cheilitis, nausea, constipation, diarrhea, abdominal pain, vomiting, inflammatory bowel disease,

hepatitis, pancreatitis, bleeding and inflammation of the gums, colitis, esophagitis, esophageal ulceration, ileitis.

Hematologic

Anemia and decreased RBC parameters, thrombocytopenia, increased platelet counts, decreased WBC counts, severe neutropenia, rare reports of agranulocytosis.

Infections and Infestations

Nasopharyngitis, hordeolum, infections (including disseminated herpes simplex and upper respiratory tract infection).

Laboratory Abnormalities

The following lab tests were increased: creatine phosphokinase (CPK), triglycerides, alanine aminotransferase (SGPT), aspartate aminotransferase (SGOT), gamma-glutamyltransferase (GGTP), cholesterol, low density lipoprotein (LDL), alkaline phosphatase, bilirubin, LDH, fasting blood glucose, uric acid, and sedimentation rate. However, high density lipoprotein (HDL) was decreased. Urine findings included increased white cells, proteinuria, microscopic or gross hematuria.

Musculoskeletal and Connective Tissue

Decreases in bone mineral density, musculoskeletal symptoms (sometimes severe) including back pain, arthralgia, musculoskeletal pain, neck pain, extremity pain, myalgia, musculoskeletal stiffness [see Warnings and Precautions (5.12)], skeletal hyperostosis, calcification of tendons and ligaments, premature epiphyseal closure, tendonitis, arthritis, transient chest pain, and rare reports of rhabdomyolysis.

Neurological

Headache, syncope, intracranial hypertension (pseudotumor cerebri), dizziness, drowsiness, lethargy, malaise, nervousness, paresthesia, seizures, stroke, weakness.

Psychiatric

Suicidal ideation, insomnia, anxiety, depression, irritability, panic attack, anger, euphoria, violent behaviors, emotional instability, suicide attempts, suicide, aggression, psychosis and auditory hallucinations. Of the patients reporting depression, some reported that the depression subsided with discontinuation of therapy and recurred with reinstitution of therapy.

Reproductive System

Abnormal menses, sexual dysfunction, including erectile dysfunction, decreased libido, decreased vaginal lubrication, and vaginal dryness.

Respiratory

Epistaxis, nasal dryness, bronchospasm (with or without a history of asthma), respiratory infection, voice alteration.

Skin and Subcutaneous Tissue

Dry skin, dermatitis, eczema, rash, contact dermatitis, alopecia, pruritus, sunburn, erythema, acne fulminans, alopecia(which in some cases persisted), bruising, dry nose, eruptive xanthomas, erythema multiforme, flushing, skin fragility, hair abnormalities, hirsutism, hyperpigmentation and hypopigmentation, nail dystrophy, paronychia, peeling of palms and soles, photoallergic/photosensitizing reactions, pruritus, pyogenic granuloma, rash (including facial erythema, seborrhea, and eczema), Stevens-Johnson syndrome, increased sunburn susceptibility, sweating, toxic epidermal necrolysis, urticaria,vasculitis (including granulomatosis with polyangiitis), abnormal wound healing (delayed healing or exuberant granulation tissue with crusting).

Senses

Hearing: tinnitus and hearing impairment.

Ocular: dry eyes, reduced visual acuity, blurred vision, eye pruritis, eye irritation, asthenopia, decreased night vision, ocular hyperemia, increased lacrimation, conjunctivitis, corneal opacities, decreased night vision which may persist, cataracts, color vision disorder, conjunctivitis, eyelid inflammation, keratitis, optic neuritis, photobia, visual disturbances.

Renal and Urinary

Glomerulonephritis.

7 DRUG INTERACTIONS

7.1 Vitamin A

ABSORICA/ABSORICA LD is closely related to vitamin A. Therefore, the use of both vitamin A and ABSORICA/ABSORICA LD at the same time may lead to vitamin A related adverse reactions. Patients treated with ABSORICA/ABSORICA LD should be advised against taking supplements containing Vitamin A to avoid additive toxic effects.

7.2 Tetracyclines

Concomitant treatment with ABSORICA/ABSORICA LD and tetracyclines should be avoided because isotretinoin use has been associated with a number of cases of intracranial hypertension (pseudotumor cerebri), some of which involved concomitant use of tetracyclines [see Warnings and Precautions (5.5)].

7.3 Phenytoin

Phenytoin is known to cause osteomalacia. No formal clinical trials have been conducted to assess if there is an interactive effect on bone loss between phenytoin and isotretinoin. Therefore, caution should be exercised when using these drugs together.

7.4 Systemic Corticosteroids

Systemic corticosteroids are known to cause osteoporosis. No formal clinical trials have been conducted to assess if there is an interactive effect on bone loss with concomitant use of systemic corticosteroids and isotretinoin. Therefore, caution should be exercised when using these drugs together.

7.5 Norethindrone/ethinyl estradiol

In a trial of 31 premenopausal female patients with severe recalcitrant nodular acne receiving norethindrone and ethinyl estradiol as an oral contraceptive agent, isotretinoin capsules within the recommended dosage, did not induce clinically relevant changes in the pharmacokinetics of ethinyl estradiol and norethindrone and in the serum levels of progesterone, follicle-stimulating hormone (FSH) and luteinizing hormone (LH). Although this study did not show any clinically significant interaction between isotretinoin and norethindrone, it is not known if there is an interaction between isotretinoin with other progestins.

8 USE IN SPECIFIC POPULATIONS

8.1 Pregnancy

Pregnancy Exposure Registry

There is a pregnancy exposure registry that monitors pregnancy outcomes in patients exposed to isotretinoin during pregnancy. Report any suspected fetal exposure during or 1 month after ABSORICA/ABSORICA LD therapy immediately to the FDA via the MedWatch telephone number 1-800-FDA-1088 and also to the iPLEDGE pregnancy registry at 1-866-495-0654 or via the internet (www.ipledgeprogram.com).

Risk Summary

ABSORICA/ABSORICA LD are contraindicated during pregnancy because isotretinoin can cause fetal harm when administered to a pregnant patient. There is an increased risk of major congenital malformations, spontaneous abortions, and premature births following isotretinoin exposure during pregnancy in humans. If ABSORICA/ABSORICA LD is used during pregnancy, or if the patient becomes pregnant while taking ABSORICA/ABSORICA LD, the patient should be apprised of the potential hazard to a fetus. If pregnancy occurs during treatment of a patient who is taking ABSORICA/ABSORICA LD, ABSORICA/ABSORICA LD must be discontinued immediately and the patient should be referred to an Obstetrician-Gynecologist experienced in reproductive toxicity for further evaluation and counseling.

Data

Human Data

Major congenital malformations that have been documented following isotretinoin exposure include malformations of the face, eyes, ears, skull, central nervous system, cardiovascular system, and thymus and parathyroid glands. External malformations include: skull; ear (including anotia, micropinna, small or absent external auditory canals); eye (including microphthalmia); facial dysmorphia and cleft palate. Internal abnormalities include: CNS (including cerebral and cerebellar malformations, hydrocephalus, microcephaly, cranial nerve deficit); cardiovascular; thymus gland; parathyroid hormone deficiency. In some cases, death has occurred as a result of the malformations.

Cases of IQ scores less than 85 with or without other abnormalities have been reported in children exposed in utero to isotretinoin. An increased risk of spontaneous abortion and premature births have been reported with isotretinoin exposure during pregnancy.

8.2 Lactation

Risk Summary

There are no data on the presence of isotretinoin in either animal or human milk, the effects on the breastfed infant, or the effects on milk production. Because of the potential for serious adverse reactions in nursing infants from isotretinoin, advise patients that breastfeeding is not recommended during treatment with ABSORICA/ABSORICA LD, and for at least 8 days after the last dose of ABSORICA/ABSORICA LD.

8.3 Females and Males of Reproductive Potential

All patients who can become pregnant must comply with the iPLEDGE program requirements [see Warnings and Precautions (5.2)].

Pregnancy Testing

ABSORICA/ABSORICA LD must only be prescribed to patients who are known not to be pregnant as confirmed by a negative CLIA-certified laboratory conducted pregnancy test. Patients who can become pregnant must have had two negative urine or serum pregnancy tests with a sensitivity of at least 25 mIU/mL before receiving the initial ABSORICA/ABSORICA LD prescription (the interval between the two tests must be at least 19 days).

- The first test (a screening test) is obtained by the prescriber when the decision is made to prescribe ABSORICA/ABSORICA LD therapy.
- The second pregnancy test (a confirmation test) is performed after the patient has used 2 forms of contraception for 1 month and during the first 5 days of the menstrual period immediately preceding the beginning of ABSORICA/ABSORICA LD therapy (for patients with regular menstrual cycles) or immediately preceding the beginning of ABSORICA/ABSORICA LD therapy (for patients with amenorrhea, irregular cycles, or using a contraceptive method that precludes withdrawal bleeding).

A pregnancy test must be repeated each month, in a CLIA-certified laboratory prior to the patient receiving each prescription. A pregnancy test must also be completed at the end of the entire course of ABSORICA/ABSORICA LD therapy and 1 month after the discontinuation of ABSORICA/ABSORICA LD.

Contraception

Patients who can become pregnant must use 2 forms of contraception simultaneously, at least 1 of which must be a primary form, for at least 1 month prior to initiation of ABSORICA/ABSORICA LD therapy, during ABSORICA/ABSORICA LD therapy, and for 1 month after discontinuing ABSORICA/ABSORICA LD therapy. However, 2 forms of contraception is not required if the patient commits to continuous abstinence from not having any sexual contact with a partner which may result in pregnancy, has undergone a hysterectomy or bilateral oophorectomy, or has been medically confirmed to be post-menopausal. Micro-dosed progesterone preparations (“minipills” that do not contain an estrogen) are an inadequate method of contraception during ABSORICA/ABSORICA LD therapy.

Primary forms | Secondary forms
•Tubal sterilization | Barrier:
•Male vasectomy | •male latex condom with or without spermicide
•Intrauterine device | •diaphragm with spermicide
•Hormonal (combination oral contraceptives, vaginal systems, vaginal inserts, transdermal systems, injections, or implants) | •cervical cap with spermicide
•Hormonal (combination oral contraceptives, vaginal systems, vaginal inserts, transdermal systems, injections, or implants) | Other:; •Vaginal sponge (contains spermicide)

Any birth control method can fail. There have been reports of pregnancy from patients who have used combination oral contraceptives, as well as contraceptive vaginal systems, vaginal inserts, transdermal systems, and injections; these pregnancies occurred while taking isotretinoin. These reports are more frequent for patients who use only a single method of contraception. Therefore, it is critically important that patients who can become pregnant use 2 methods of contraception simultaneously.

A clinical drug interaction study did not show any clinically significant interaction between isotretinoin and norethindrone and ethinyl estradiol; however, it is not known if there is an interaction between isotretinoin with other progestins [see

Drug Interactions (7.5)]. Prescribers are advised to consult the prescribing information of any medication administered concomitantly with hormonal contraceptives, since some medications may decrease the effectiveness of these birth control products.

Patients who can become pregnant should be prospectively cautioned not to self-medicate with the herbal supplement St. John’s Wort because of a possible interaction with hormonal contraceptives based on reports of breakthrough bleeding on oral contraceptives shortly after starting St. John’s Wort. Pregnancies have been reported by users of combined hormonal contraceptives who also used some form of St. John’s Wort.

If the patient has unprotected sexual contact with a partner that could result in pregnancy at any time 1 month before, during, or 1 month after therapy, the patient must:

1. Stop taking ABSORICA/ABSORICA LD immediately, if on therapy
2. Have a pregnancy test at least 19 days after the last act of unprotected sexual contact with a partner that could result in pregnancy
3. Start using 2 forms of contraception simultaneously again for 1 month before resuming ABSORICA/ABSORICA LD therapy
4. Have a second pregnancy test after using 2 forms of contraception for 1 month.

Infertility

In a trial of female acne patients (n = 79) receiving another isotretinoin capsule product, the mean total ovarian volume, the total antral follicle count and mean anti-Mullerian hormone decreased at the end of the treatment (sixth month). However, the values returned to normal at the 18th month (12 months after the end of treatment). There were no statistically significant changes in terms of follicle-stimulating hormone and luteinizing hormone, both at the end of the treatment and 12 months after the end of treatment. Although the results suggest that possible deteriorative effects of isotretinoin on ovarian reserve may be reversible, the study has important methodological limitations, including a small sample size, lack of a control group, and lack of generalizability.

Sperm Study

In trials of 66 men, 30 of whom were patients with nodular acne under treatment with oral isotretinoin, no significant changes were noted in the count or motility of spermatozoa in the ejaculate. In a study of 50 men (ages 17 to 32 years) receiving isotretinoin therapy for nodular acne, no significant effects were seen on ejaculate volume, sperm count, total sperm motility, morphology or seminal plasma fructose.

8.4 Pediatric Use

The safety and effectiveness of ABSORICA/ABSORICA LD for the treatment of severe recalcitrant nodular acne have been established in pediatric subjects ages 12 to 17 years. Use of ABSORICA/ABSORICA LD in this age group for this indication is supported by evidence from a clinical trial (Study 1) that compared the use ABSORICA to another isotretinoin capsule product in 397 pediatric subjects (12 to 17 years) [see Clinical Studies (14)] and pharmacokinetic data in pediatric subjects [see Clinical Pharmacology (12.3)].

The safety and effectiveness of ABSORICA/ABSORICA LD in pediatric patients less than 12 years of age have not been established.

Adverse Reactions in Pediatric Subjects

In trials with isotretinoin capsules, adverse reactions reported in pediatric subjects aged 12 to 17 years old were similar to those described in adults except for the increased incidence of back pain and arthralgia (both of which were sometimes severe) and myalgia in pediatric subjects. In a trial of pediatric subjects aged 12 to 17 years old treated with isotretinoin capsules, approximately 29% (104/358) developed back pain. Back pain was severe in 14% (14/104) of the cases and occurred at a higher frequency in female subjects than male subjects. Arthralgias were experienced in 22% (79/358) of pediatric subjects including severe arthralgias in 8% (6/79) of subjects. Appropriate evaluation of the musculoskeletal system should be done in adolescents who present with these symptoms during or after a course of ABSORICA/ABSORICA LD. Consider discontinuing ABSORICA/ABSORICA LD if any significant abnormality is found.

Effects on Bone Mineral Density in Pediatric Subjects

The effect on bone mineral density (BMD) of a 20-week course of therapy with ABSORICA or another isotretinoin capsule product was evaluated in a double-blind, randomized clinical trial involving 396 adolescents with severe recalcitrant nodular acne (mean age 15.4 years old, range 12 to 17 years old, 80% males). Given that there were no statistically significant differences between the two isotretinoin capsule groups following 20 weeks of treatment, the results are presented for the pooled treatment groups. The mean changes in BMD from baseline for the overall trial population were 1.8% for lumbar spine, -0.1% for total hip and -0.3% for femoral neck. Mean BMD Z-scores declined from baseline at each of these sites (-0.053, -0.109 and -0.104 respectively). Out of 306 adolescents, 27 (9%) had clinically significant BMD declines defined as ≥4% lumbar spine or total hip, or ≥5% femoral neck, including 2 subjects for lumbar spine, 17 for total hip and 20 for femoral neck. Repeat DXA scans within 2 to 3 months after the post treatment scan showed no recovery of BMD. Long-term follow-up at 4 to 11 months showed that 3 out of 7 subjects had total hip and femoral neck BMD below pre-treatment baseline, and 2 others did not show the increase in BMD above baseline expected in this adolescent population. The significance of these changes in regard to long-term bone health and future fracture risk is unknown [see Warnings and Precautions (5.12)].

In an open-label clinical trial (N=217) of a single course of therapy with isotretinoin capsules for adolescents with severe recalcitrant nodular acne, BMD at several skeletal sites were not significantly decreased (lumbar spine change >-4% and total hip change >-5%) or were increased in the majority of subjects. One patient had a decrease in lumbar spine BMD >4% based on unadjusted data. Sixteen (8%) subjects had decreases in lumbar spine BMD >4%, and all the other subjects (92%) did not have significant decreases or had increases (adjusted for body mass index). Nine subjects (5%) had a decrease in total hip BMD >5% based on unadjusted data. Twenty-one (11%) subjects had decreases in total hip BMD >5%, and all the other subjects (89%) did not have significant decreases or had increases (adjusted for body mass index). Follow-up trials performed in 8 of the subjects with decreased BMD for up to 11 months thereafter demonstrated increasing BMD in 5 subjects at the lumbar spine, while the other 3 subjects had lumbar spine BMD measurements below baseline values. Total hip BMD remained below baseline (range −1.6% to −7.6%) in 5 of 8 subjects (63%).

In a separate open-label extension trial of 10 subjects including those ages 13 to 17 years, who started a second course of isotretinoin capsules 4 months after the first course, two subjects showed a decrease in mean lumbar spine BMD up to 3.3%.

Epiphyseal Closure

There are reports of premature epiphyseal closure in acne patients who used isotretinoin at recommended doses. The effect of multiple courses of isotretinoin on epiphyseal closure is unknown. In a 20-week clinical trial that included 289 adolescents who had hand radiographs taken to assess bone age, a total of 9 subjects had bone age changes that were clinically significant and for which an isotretinoin-related effect cannot be excluded [see Warnings and Precautions (5.12)].

8.5 Geriatric Use

Clinical studies of ABSORICA/ABSORICA LD did not include sufficient numbers of geriatric subjects (subjects aged 65 years of age and older) to determine whether they respond differently from younger adults. Although reported clinical experience has not identified differences in responses between geriatric and younger adults, effects of aging may increase some risks associated with ABSORICA/ABSORICA LD therapy.

10 OVERDOSAGE

In humans, isotretinoin overdosage has been associated with vomiting, facial flushing, cheilosis, abdominal pain, headache, dizziness, and ataxia. These symptoms quickly resolved without apparent residual effects.

Patients who can become pregnant who present with an ABSORICA/ABSORICA LD overdosage should be evaluated for pregnancy. Because an overdosage would be expected to result in higher levels of isotretinoin in semen than found during a normal treatment course, male patients treated with ABSORICA/ABSORICA LD should use a condom, or avoid reproductive sexual activity with a patient who is or might become pregnant, for 1 month after the overdose.

All patients with ABSORICA/ABSORICA LD overdose should not donate blood for at least 1 month.

11 DESCRIPTION

ABSORICA

ABSORICA (isotretinoin) Capsules contain 10 mg, 20 mg, 25 mg, 30 mg, 35 mg or 40 mg of isotretinoin (a retinoid) in hard gelatin capsules for oral administration. In addition to the active ingredient, isotretinoin, each capsule contains the following inactive ingredients: propyl gallate, sorbitan monooleate, soybean oil and stearoyl polyoxylglycerides. The gelatin capsules contain the following dye systems:

•10 mg – iron oxide (yellow) and titanium dioxide;

•20 mg – iron oxide (red), and titanium dioxide;

•25 mg – FD&C Blue #1, FD&C Yellow #5 [see Warnings and Precautions (5.14)], FD&C Yellow #6 and titanium dioxide;

•30 mg – iron oxide (black, red and yellow) and titanium dioxide;

•35 mg – FD&C Blue #2, iron oxide (black, red and yellow) and titanium dioxide;

•40 mg – iron oxide (black, red and yellow) and titanium dioxide.

ABSORICA LD

ABSORICA LD (isotretinoin) Capsules contain 8 mg, 16 mg, 20 mg, 24 mg, 28 mg and 32 mg of micronized isotretinoin (a retinoid) in suspension filled in hard gelatin capsules for oral administration. In addition to the active ingredient, isotretinoin, USP each capsule contains the following inactive ingredients: butylated hydroxy anisole, gelatin, hard gelatin capsule shell, polysorbate 80 and soybean oil. The gelatin capsules contain the following dye systems:

•8 mg – D&C Yellow #10, FD&C Blue #1, FD&C Red #40 and titanium dioxide

•16 mg – FD&C Blue #1, FD&C Red #40, and titanium dioxide

•20 mg – FD&C Blue #1, FD&C Red #40, and titanium dioxide

•24 mg – D&C Yellow #10, FD&C Yellow #6 and titanium dioxide

•28 mg – FD&C Blue #1, FD&C Red #40, and titanium dioxide

•32 mg – ferrosoferric oxide, ferric oxide (red and yellow) and titanium dioxide

The imprinting ink of 8 mg, 16 mg, 24 mg and 32 mg capsules contain the following ingredients: potassium hydroxide, propylene glycol, shellac and titanium dioxide.

The imprinting ink of 20 mg and 28 mg capsules contain the following ingredients: ferrosoferric oxide, propylene glycol and shellac glaze.

Isotretinoin

Chemically, isotretinoin is 13-cis-retinoic acid and is related to both retinoic acid and retinol (vitamin A). It is a yellow to orange crystalline powder with a molecular weight of 300.44. It is practically insoluble in water, soluble in chloroform and sparingly soluble in alcohol and in isopropyl alcohol. The structural formula is:

ABSORICA meets USP Dissolution Test 3.

For ABSORICA LD, FDA approved dissolution test differs from the USP.

12 CLINICAL PHARMACOLOGY

12.1 Mechanism of Action

ABSORICA/ABSORICA LD is a retinoid, which when administered at the recommended dosage [see Dosage and Administration (2.1)], inhibits sebaceous gland function and keratinization. Clinical improvement in nodular acne patients occurs in association with a reduction in sebum secretion. The decrease in sebum secretion is temporary and is related to the dose and duration of treatment with isotretinoin capsules and reflects a reduction in sebaceous gland size and an inhibition of sebaceous gland differentiation. The exact mechanism of action of ABSORICA/ABSORICA LD in the treatment of severe recalcitrant nodular acne is unknown.

12.2 Pharmacodynamics

The pharmacodynamics of ABSORICA/ABSORICA LD are unknown.

12.3 Pharmacokinetics

No clinically significant differences in the pharmacokinetics of isotretinoin between patients with nodular acne and healthy subjects without acne were reported in published literature.

Absorption Following ABSORICA Administration

The ABSORICA mean Tmax was 6.4 hours under fed conditions and 2.9 hours under fasting conditions following administration of a single 40 mg dose.

Effect on Food

No clinically significant differences in ABSORICA pharmacokinetics were observed following administration with a modified high-fat, high-calorie meal (123.2 calories from protein, 265.6 calories from carbohydrates, and 468 calories from fat; total calories 857 calories) with reduced vitamin A content. The mean AUC0-t and Cmax of isotretinoin were 6095 ng*hr/mL and 369 ng/mL, respectively, following administration of a single 40 mg ABSORICA dose under fed conditions; which were approximately 50% and 26% higher, respectively, compared to fasting conditions. However, ABSORICA may be given with or without meals [see Dosage and Administration (2.1)].

Absorption Following ABSORICA LD Administration

The ABSORICA LD median Tmax was 5 hours under fed conditions and 3.5 hours under fasting conditions following administration of a single 32 mg dose.

Effect on Food

No clinically significant differences in ABSORICA LD pharmacokinetics were observed following administration with a high-fat, high-calorie meal (150 calories from protein, 250 calories from carbohydrates, and 500 calories from fat; total calories 900 calories). The mean AUC0-t and Cmax of isotretinoin were 10209 ng*hr/mL and 646 ng/mL, respectively, following administration of a single 32 mg ABSORICA LD dose under fed conditions; which were approximately 20% and 6% higher, respectively, compared to fasting conditions. However, ABSORICA LD may be given with or without meals [see Dosage and Administration (2.1)].

Distribution

Isotretinoin is more than 99.9% bound to plasma proteins, primarily albumin.

Elimination

The mean elimination half-lives of isotretinoin and its 4-oxo-isotretinoin metabolite were:

•18 hours and 38 hours, respectively, after a single oral ABSORICA 40 mg dose.

•Approximately 24 hours and 38 hours, respectively, after a single oral ABSORICA LD 32 mg dose.

Metabolism: Isotretinoin is primarily metabolized by CYP2C8, 2C9, 3A4, and 2B6 in vitro. Isotretinoin and its metabolites are further metabolized into conjugates.

Following oral administration of isotretinoin capsules, at least three metabolites (4-oxo-isotretinoin, retinoic acid (tretinoin), and 4-oxo-retinoic acid (4-oxo-tretinoin)) have been identified in human plasma. The extent of formation of all metabolites was higher under fed conditions. All of these metabolites possess retinoid activity in vitro. The clinical significance is unknown.

Excretion: Following oral administration of an 80 mg dose of radiolabeled-isotretinoin as a liquid suspension, the metabolites of isotretinoin were excreted in feces and urine in relatively equal amounts (total of 65% to 83%).

Specific Populations

Pediatric Patients: No clinically significant differences in the pharmacokinetics of isotretinoin were observed based on age (12 to 15 years (n=38), and ≥18 years (n=19)). In both age groups, 4-oxo-isotretinoin was the major metabolite; tretinoin and 4-oxo-tretinoin were also observed [see Use in Specific Populations (8.4)].

Drug Interaction Studies

No clinically significant differences in the pharmacokinetics of phenytoin (CYP2C9 substrate) were observed when used concomitantly with isotretinoin.

13 NONCLINICAL TOXICOLOGY

13.1 Carcinogenesis, Mutagenesis and Impairment of Fertility

In male and female Fischer 344 rats given oral isotretinoin at dosages of 8 or 32 mg/kg/day (1.3 or 5.3 times the recommended clinical ABSORICA dosage of 1 mg/kg/day or the recommended clinical ABSORICA LD dosage of 0.8 mg/kg/day, respectively, after normalization for total body surface area) for greater than 18 months, there was a dose-related increased incidence of pheochromocytoma relative to controls. The incidence of adrenal medullary hyperplasia was also increased at the higher dosage in both sexes. The relatively high level of spontaneous pheochromocytomas occurring in the male Fischer 344 rat makes it an equivocal model for study of this tumor; therefore, the relevance of this tumor to humans is uncertain.

The Ames test was conducted with isotretinoin in two laboratories. The results of the tests in one laboratory were negative, while in the second laboratory, a weakly positive response (less than 1.6 times background) was noted in S. typhimurium TA100 when the assay was conducted with metabolic activation. No dose response effect was seen, and all other strains were negative. Additionally, other tests designed to assess genotoxicity (Chinese hamster cell assay, mouse micronucleus test, S. cerevisiae D7 assay, in vitro clastogenesis assay with human-derived lymphocytes, and unscheduled DNA synthesis assay) were all negative.

In rats, no adverse effects on gonadal function, fertility, conception rate, gestation or parturition were observed at oral dosages of isotretinoin of 2, 8, or 32 mg/kg/day (0.3, 1.3, or 5.3 times the recommended clinical ABSORICA dosage of 1 mg/kg/day or the recommended clinical ABSORICA LD dosage of 0.8 mg/kg/day, respectively, after normalization for total body surface area).

In dogs, testicular atrophy was noted after treatment with oral isotretinoin for approximately 30 weeks at dosages of 20 or 60 mg/kg/day (10 or 30 times the recommended clinical ABSORICA dosage of 1 mg/kg/day or the recommended clinical ABSORICA LD dosage of 0.8 mg/kg/day, respectively, after normalization for total body surface area). In general, there was microscopic evidence for appreciable depression of spermatogenesis, but some sperm were observed in all testes examined, and in no instance were completely atrophic tubules seen.

13.2 Animal Toxicology

In rats given 8 or 32 mg/kg/day of isotretinoin (1.3 or 5.3 times the recommended clinical ABSORICA dosage of 1 mg/kg/day or the recommended clinical ABSORICA LD dosage of 0.8 mg/kg/day, respectively, after normalization for total body surface area) for 18 months or longer, the incidences of focal calcification, fibrosis and inflammation of the myocardium, calcification of coronary, pulmonary and mesenteric arteries, and metastatic calcification of the gastric mucosa were greater than in control rats of similar age. Focal endocardial and myocardial calcifications associated with calcification of the coronary arteries were observed in two dogs after approximately 6 to 7 months of treatment with isotretinoin at a dosage of 60 to 120 mg/kg/day (30 to 60 times the recommended clinical ABSORICA dosage of 1 mg/kg/day or the recommended clinical ABSORICA LD dosage of 0.8 mg/kg/day, respectively, after normalization for total body surface area).

14 CLINICAL STUDIES

The effectiveness of ABSORICA/ABSORICA LD for the treatment of severe recalcitrant nodular acne in patients 12 years of age and older has been established and is based on a double-blind, randomized, parallel group trial (Study 1) in subjects with severe recalcitrant nodular acne who received ABSORICA or another isotretinoin capsule product under fed conditions. A total of 925 subjects were randomized 1:1 to receive ABSORICA or another isotretinoin capsule product. Study subjects ranged from 12 to 54 years of age (including 397 pediatric subjects 12 to 17 years old); 60% were male, 40% were female; and the racial groups included 87% White, 4% Black, 6% Asian, and 3% Other. Enrolled subjects had a weight of 40 to 110 kg and had at least 10 nodular lesions on the face and/or trunk. Subjects were treated with an initial dose of 0.5 mg/kg/day in two divided doses for the first 4 weeks, followed by 1 mg/kg/day in two divided doses for the following 16 weeks.

Change from baseline to Week 20 in total nodular lesion count and proportion of subjects with at least a 90% reduction in total nodular lesion count from baseline to Week 20 are presented in Table 3. Total nodular lesion counts by visit are presented in Figure 1. A single course of ABSORICA and another isotretinoin capsule product therapy for 15 to 20 weeks has been shown to result in complete and prolonged remission of acne in many patients.

Table 3: Efficacy Results in Subjects with Severe Recalcitrant Nodular Acne at Week 20 (Study 1)

 | ABSORICA; N=464 | Another; Isotretinoin; Capsule Product*; N=461
Nodular Lesions; Mean Baseline Count; Mean Reduction | 18.4; -15.68 | 17.7; -15.62
Subjects Achieving 90% Reduction, n (%) | 324 (70%) | 344 (75%)

Figure 1: Total Nodular (Facial and Truncal) Lesion Count in Subjects with Severe Recalcitrant Nodular Acne by Visit in Study 1

* Another isotretinoin capsule product.

15 REFERENCES

1.Cinar SL, Kartal D, Aksoy H, et al. Long-term effect of systemic isotretinoin on female fertility. Cutan Ocul Toxicol. 2017;36(2):132-134.

16 HOW SUPPLIED/STORAGE AND HANDLING

ABSORICA and ABSORICA LD have different dosage regimens. Although ABSORICA and ABSORICA LD have a 20 mg strength, these strengths have different bioavailability and are not substitutable [see Dosage and Administration (2.1)].

ABSORICA

ABSORICA (isotretinoin) Capsules (opaque) are supplied as follows:

- 10 mg: Dark yellow, capsule imprinted with black ink “G 240” on cap and “10” on the body
- Box of 30 capsules (3 x 10 Prescription Packs): NDC 10631-115-31
- 20 mg: Red, capsule imprinted with black ink “G 241” on cap and “20” on the body
- Box of 30 capsules (3 x 10 Prescription Packs): NDC 10631-116-31
- 25 mg: Green, capsule imprinted with white ink “G 342” on cap and “25” on the bodyBox of 30 capsules (3 x 10 Prescription Packs): NDC 10631-133-31
- 30 mg: Brown, capsule imprinted with white ink “G 242” on cap and “30” on the bodyBox of 30 capsules (3 x 10 Prescription Packs): NDC 10631-117-31
- 35 mg: Dark blue, capsule imprinted with white ink “G 343” on cap and “35” on the bodyBox of 30 capsules (3 x 10 Prescription Packs): NDC 10631-134-31
- 40 mg: Brown and red, capsule imprinted with white ink “G 325” on cap and “40” on the bodyBox of 30 capsules (3 x 10 Prescription Packs): NDC 10631-118-31

ABSORICA LD

ABSORICA LD (isotretinoin) Capsules (opaque-printed, hard-gelatin) are supplied as follows:

- 8 mg: A size 3, light green, capsules banded with a colorless band. The cap is printed in white with “RL29” and the body is printed in white with “RL29”.

Box of 30 capsules (3 x 10 Prescription Packs) NDC 10631-002-31

- 16 mg: A size 2, dark blue, capsules banded with a colorless band. The cap is printed in white with “RL30” and the body is printed in white with “RL30”.

Box of 30 capsules (3 x 10 Prescription Packs) NDC 10631-003-31

- 20 mg: A size 1, dark pink, capsules banded with a colorless band. The cap is printed in black with “RL33”and the body is printed in black with “RL33”.

Box of 30 capsules (3 x 10 Prescription Packs) NDC 10631-004-31

- 24 mg: A size 1, yellow, capsules banded with a colorless band. The cap is printed in white with “RL31” and the body is printed in white with “RL31”.

Box of 30 capsules (3 x 10 Prescription Packs) NDC 10631-005-31

- 28 mg: A size 0, light blue, capsules banded with a colorless band. The cap is printed in black with “RL34” and the body is printed in black with “RL34”.

Box of 30 capsules (3 x 10 Prescription Packs) NDC 10631-006-31

- 32 mg: A size 0, caramel, capsules banded with a colorless band. The cap is printed in white with “RL32” and the body is printed in white with “RL32”.

Box of 30 capsules (3 x 10 Prescription Packs): NDC 10631-007-31

Storage and Handling of ABSORICA and ABSORICA LD

Store at 20°C to 25°C (68°F to 77°F), excursions permitted between 15°C to 30°C (59°F to 86°F) [see USP controlled room temperature]. Protect from light.

17 PATIENT COUNSELING INFORMATION

Advise the patient to read the FDA-approved patient labeling (Medication Guide).

Embryo-Fetal Toxicity

There is an extremely high risk of life-threatening birth defects when ABSORICA/ABSORICA LD is used in pregnancy [see Warnings and Precautions (5.1) and Use in Specific Populations (8.1)]. Instruct patients who can become pregnant that they must not be pregnant during or up to one month after ABSORICA/ABSORICA LD therapy. Instruct patients to not donate blood during ABSORICA/ABSORICA LD therapy and for 1 month following discontinuation to avoid blood donation to a pregnant patient.

iPLEDGE

ABSORICA and ABSORICA LD are available only through a restricted program called iPLEDGE [see Warnings and Precautions (5.2)]. Inform patients who can become pregnant of the following notable requirements. These patients must:

- Sign an informed consent form to be enrolled in the program
- Comply with the pregnancy testing and contraception requirements [see Use in Specific Populations (8.3)]
- Demonstrate comprehension of the safe-use conditions of the program every month
- Obtain the prescription within 7 days of the pregnancy test collection

Inform patients who cannot become pregnant of the following notable requirements. These patients must sign an informed consent form to enroll in the program and they must obtain the prescription within 30 days of the office visit. ABSORICA/ABSORICA LD is available only from certified pharmacies participating in the program. Therefore, provide patients with the telephone number and website for information on how to obtain ABSORICA/ABSORICA LD [see Warnings and Precautions (5.2)].

Lactation

Because of the potential for serious adverse reactions in nursing infants from isotretinoin, advise patients that breastfeeding is not recommended during treatment with ABSORICA/ABSORICA LD, and for at least 8 days after the last dose of ABSORICA/ABSORICA LD [see Use in Specific Populations (8.2)].

Psychiatric Disorders

Instruct patients and/or their caregivers/families that ABSORICA/ABSORICA LD may cause depression, psychosis, suicidal ideation, suicide attempts, and aggressive or violent behavior. Instruct patients to read the Recognizing Psychiatric Disorders in Adolescents and Young Adults brochure prior to taking ABSORICA/ABSORICA LD. Instruct patients to stop ABSORICA/ABSORICA LD and to contact a healthcare provider if they develop any of these signs or symptoms [see Warnings and Precautions (5.4)].

Important Administration Instructions

To decrease the risk of esophageal irritation, instruct patients to swallow the capsules with a full glass of liquid [see

Dosage and Administration (2.1)].

Intracranial Hypertension (Pseudotumor Cerebri)

Advise patients that intracranial hypertension (pseudotumor cerebri) has occurred with ABSORICA/ABSORICA LD use including concomitant use with tetracyclines. Thus, advise patients to avoid concomitant use with tetracyclines and to discontinue ABSORICA/ABSORICA LD immediately if they have symptoms of intracranial hypertension [see Warningsand Precautions (5.5)].

Serious Skin Reactions

Advise patients that severe skin reactions (Stevens-Johnson syndrome and toxic epidermal necrolysis) have been reported in patients treated with isotretinoin and to discontinue ABSORICA/ABSORICA LD if clinically significant skin reactions occur [see Warnings and Precautions (5.6)].

Inflammatory Bowel Disease

Advise patients that inflammatory bowel disease (including regional ileitis) have occurred with isotretinoin use including those without a prior history of IBD and if they experience IBD symptoms, they should discontinue

ABSORICA/ABSORICA LD immediately [see Warnings and Precautions (5.11)].

Musculoskeletal Abnormalities

Inform patients that:

- There have been reports of osteoporosis and fractures and that isotretinoin may have a negative effect on bone mineral density [see Warnings and Precautions (5.12)].
- Isotretinoin use has been associated with musculoskeletal abnormalities (e.g., arthralgia, back pain) [see Warnings and Precautions (5.12)].

Inform adolescents and their families that isotretinoin use in adolescents who participated in sports with repetitive impact increase their risk of spondylolisthesis or hip growth plate injuries [see Warnings and Precautions (5.12)]. Inform pediatric patients and their caregivers that pediatric patients treated with isotretinoin capsules developed back pain including severe back pain, and arthralgias including severe arthralgias [see Use in Specific Populations (8.4)].

Ocular Abnormalities

Inform patients that they may experience dry eyes, corneal opacities, and decreased night vision and contact lens wearers may experience decreased tolerance to contact lenses during and after therapy [see Warnings and Precautions (5.13)].

Rhabdomyolysis

Inform patients there have been rare postmarketing reports of rhabdomyolysis in patients treated with isotretinoin capsules, some associated with strenuous physical activity [see Warnings and Precautions (5.15)].

Hypersensitivity Reactions

Given that anaphylactic reactions and other allergic reactions have been reported in patients treated with isotretinoin capsules, instruct the patient to discontinue ABSORICA/ABSORICA LD and contact their healthcare provider if they have a severe allergic reaction [see Warnings and Precautions (5.14)].

Lipid Abnormalities

Instruct patients that hypertriglyceridemia, decreased HDL, and increased cholesterol levels were reported in patients treated with isotretinoin capsules [see Warnings and Precautions (5.8)].

Additional Instructions

Inform patients:

- To not share ABSORICA/ABSORICA LD with anyone else because of the risk of birth defects and other serious adverse reactions.
- That transient exacerbation (flare) of acne has been seen, generally during the initial period of therapy.
- That wax epilation and skin resurfacing procedures (such as dermabrasion, laser) should be avoided during ABSORICA/ABSORICA LD therapy and for at least 6 months thereafter due to the possibility of scarring.
- To avoid prolonged exposure to UV rays or sunlight.

Distributed by:
Sun Pharmaceutical Industries, Inc.
Cranbury, NJ 08512

ABSORICA and ABSORICA LD are registered trademarks of Sun Pharmaceutical Industries, Inc. All other trademarks are property of their respective owners.

ABSORICA LD 8 mg, 16 mg, 20 mg, 24 mg, 28 mg and 32 mg is protected by US Patent No. US 9,700,535 and US 9,750,711.

Medication Guide

ABSORICA (ab-sore-i-kah)

(isotretinoin) capsules

ABSORICA (ab-sore-i-kah) LD

(isotretinoin) capsules

IMPORTANT: ABSORICA LD is not the same as ABSORICA or other isotretinoin generic products. Do not change between ABSORICA LD and ABSORICA or other isotretinoin generic products.

Read the Medication Guide that comes with ABSORICA or ABSORICA LD before you start taking it and each time you get a prescription. There may be new information. This information does not take the place of talking with your healthcare provider about your medical condition or your treatment.

What is the most important information I should know about ABSORICA and ABSORICA LD?

•ABSORICA and ABSORICA LD can harm your unborn baby, including birth defects (deformed babies), loss of a baby before birth (miscarriage), death of the baby, and early (premature) births. Patients who are pregnant or who plan to become pregnant must not take ABSORICA or ABSORICA LD.

Patients must not get pregnant:

•for 1 month before starting ABSORICA or ABSORICA LD

•during treatment with ABSORICA or ABSORICA LD

•for 1 month after stopping ABSORICA or ABSORICA LD

If you get pregnant during treatment with ABSORICA orABSORICALD, stop taking it right away and call your healthcare provider. Healthcare providers and patients should report all cases of pregnancy during treatment or 1 month after stopping treatment to:

•FDA MedWatch at 1-800-FDA-1088, and

•the iPLEDGE Pregnancy Registry at 1-866-495-0654 or www.ipledgeprogram.com

Because ABSORICA and ABSORICA LD can cause birth defects, ABSORICA and ABSORICA LD are only for patients who can understand and agree to carry out all of the instructions in the iPLEDGE Program.

•Serious mental health problems, including:

•depression

•psychosis (seeing or hearing things that are not real)

•suicide. Some patients taking ABSORICA or ABSORICA LD have had thoughts about hurting themselves or putting an end to their own lives (suicidal thoughts). Some people tried to end their own lives. Some people have ended their own lives.

Stop taking ABSORICA or ABSORICALD and call your healthcare provider right away if you or a family member notices that you have any of the following signs and symptoms of depression or psychosis:

Your healthcare provider may tell you to see a mental healthcare professional if you had any of these symptoms.

What are ABSORICA and ABSORICALD?

ABSORICA and ABSORICA LD are prescription medicines used in patients 12 years of age and older, who are not pregnant, for the treatment of severe acne (nodular acne) that cannot be cleared up by any other acne treatments, including antibiotics. ABSORICA and ABSORICA LD can cause serious side effects (see “What is the most important information I should know about ABSORICA and ABSORICALD?”).

ABSORICA and ABSORICA LD can only be:

•prescribed by healthcare providers that are registered in the iPLEDGE Program

•dispensed by a pharmacy that is registered with the iPLEDGE Program

•given to patients who are registered in the iPLEDGE Program and agree to do everything required in the program.

It is not known if ABSORICA and ABSORICA LD are safe and effective in children less than 12 years of age.

Do not take ABSORICA or ABSORICALD if you:

1.are pregnant, plan to become pregnant, or become pregnant during ABSORICA and ABSORICALD treatment. ABSORICA and ABSORICA LD cause severe birth defects. See “What is the most important information I should know about ABSORICA and ABSORICALD?”

2.are allergic to isotretinoin, vitamin A, or any of the ingredients in ABSORICA and ABSORICA LD.

See the end of this Medication Guide for a complete list of ingredients in ABSORICA and ABSORICA LD.

Before taking ABSORICA or ABSORICALD, tell your healthcare provider if you or a family member has any of the following health conditions:

1.mental health problems

2.asthma

3.liver problems

4.diabetes

5.heart disease

6.increase blood fat levels (cholesterol and triglycerides)

7.bone loss (osteoporosis), weak bones or any other bone problems

8.an eating problem called anorexia nervosa (where people eat too little)

9.food or medicine allergies, including aspirin or tartrazine

Tell your healthcare provider if you are pregnant or breastfeeding. Do not breastfeed during treatment or for at least 8 days after the last dose of ABSORICA or ABSORICA LD.

Tell your healthcare provider about all of the medicines you take including prescription and over-the-counter medicines, vitamins and herbal supplements, including St. John’s wort. ABSORICA and ABSORICA LD and certain other medicines can affect each other, sometimes causing serious side effects.

Do not take the following medicines during treatment with ABSORICA or ABSORICA LD:

•vitamin A supplements

•tetracycline antibiotics

Know the medicines you take. Keep a list of them to show to your healthcare provider and pharmacist. Do not take any new medicine without talking with your healthcare provider.

How should I take ABSORICA and ABSORICALD?
You must take ABSORICA and ABSORICA LD exactly as prescribed. You must also follow all the instructions of the iPLEDGE Program. Before prescribing ABSORICA or ABSORICA LD, your healthcare provider will:

1.explain the iPLEDGE Program to you

2.have you sign the Patient Information/Informed Consent form (for all patients). Patients who can get pregnant must also sign another consent form.

3.give you a pregnancy test to make sure you are not pregnant before you start ABSORICA or ABSORICA LD. You will receive 2 pregnancy tests at least 19 days apart.

You will not be prescribed ABSORICA or ABSORICALD if you cannot agree to or follow all the instructions of the iPLEDGE Program.

•You will get no more than a 30-day supply of ABSORICA or ABSORICA LD at a time. This is to make sure you are following the ABSORICA and ABSORICA LD iPLEDGE Program.

•The amount of ABSORICA or ABSORICA LD you take has been specially chosen for you. It is based on your body weight and may change during treatment.

•Take ABSORICA or ABSORICA LD 2 times a day with or without meals, unless your healthcare provider tells you otherwise. Swallow your ABSORICA or ABSORICA LD capsules whole with a full glass of liquid. Do not chew or suck on the capsule. ABSORICA and ABSORICA LD can hurt the tube that connects your mouth to your stomach (esophagus) if not swallowed whole.

•Your healthcare provider will tell you how long you will receive treatment with ABSORICA or ABSORICA LD. Your acne may continue to improve after treatment.

•If you miss a dose, just skip that dose. Do not take two doses at the same time.

•If you take too much ABSORICA or ABSORICA LD, call your healthcare provider or poison control center right away.

•Your acne may get worse when you first start taking ABSORICA or ABSORICA LD. This should last only a short while. Talk with your healthcare provider if this is a concern for you.

•You must return to your healthcare provider as directed to make sure you don’t have signs of serious side effects. Your healthcare provider may do blood tests to check for serious side effects from ABSORICA or ABSORICA LD and may stop treatment if you get certain side effects.

•Patients who can get pregnant will get a pregnancy test each month, after you finish your course of treatment, and 1 month after you stop treatment with ABSORICA or ABSORICA LD.

•Patients who can get pregnant must use two separate forms of birth control at the same time for at least 1 month before, during treatment, and for 1 month after treatment with ABSORICA or ABSORICA LD. You must access the iPLEDGE Program system to answer questions about the program requirements and to enter your two chosen forms of birth control. To access the iPLEDGE Program system, go to www.ipledgeprogram.com or call 1-866-495-0654.

Talk about birth control options with your healthcare provider or go for a free visit to talk about birth control with another healthcare provider or family planning expert. Your healthcare provider can arrange this free visit, which will be paid for by the company that makes ABSORICA and ABSORICA LD.

If you have sex at any time without using two forms of birth control 1 month before, during, or 1 month after treatment, get pregnant, or miss your expected period, stop taking ABSORICA orABSORICALD and call your healthcare provider right away.

What should I avoid while taking ABSORICA orABSORICALD?

1.Do not give blood during treatment with ABSORICA or ABSORICA LD and for one month after stopping ABSORICA or ABSORICA LD. If someone who is pregnant gets your donated blood, their baby may be exposed to isotretinoin and may be born with birth defects.

2.Do not take other medicines or herbal products with ABSORICA or ABSORICA LD unless you talk to your healthcare provider. See “Before taking ABSORICA or ABSORICALD”

3.Do not drive at night until you know if ABSORICA or ABSORICALD has affected your vision. ABSORICA and ABSORICA LD may decrease your ability to see in the dark.

4.Do not have cosmetic procedures to smooth your skin, including waxing, dermabrasion, or laser procedures, during treatment withABSORICA or ABSORICALD and for at least 6 months after you stop. ABSORICA and ABSORICA LD can increase your chance of scarring from these procedures. Check with your healthcare provider for advice about when you can have cosmetic procedures.

5.Avoid sunlight and ultraviolet lights as much as possible. Tanning machines use ultraviolet lights. ABSORICA and ABSORICA LD may make your skin more sensitive to light.

6.Do not share ABSORICA or ABSORICALD with other people.ABSORICA and ABSORICA LD can cause birth defects and other serious health problems.

What are the possible side effects of ABSORICA and ABSORICALD?

ABSORICA and ABSORICA LD can cause serious side effects, including:

1.See “What is the most important information I should know about ABSORICA and ABSORICA LD”?

2.increased pressure in the brain (intracranial hypertension). ABSORICA and ABSORICA LD can increase the pressure in your brain. This can lead to permanent loss of eyesight, and in rare cases, death. Stop taking ABSORICA or ABSORICA LD and call your healthcare provider right away if you get any of these signs of increased brain pressure:

3.serious skin problems. Skin rash can occur in patients taking ABSORICA or ABSORICA LD. Sometimes rash can be serious and may lead to death. Stop using ABSORICA or ABSORICA LD and call your healthcare provider right away if you get:

4.inflammation of your pancreas (pancreatitis) can happen in patients who take ABSORICA or ABSORICA LD and can lead to death. Call your healthcare provider right away if you have any of the following symptoms of pancreatitis:

5.increased blood fat (lipid) levels. ABSORICA and ABSORICA LD can raise blood fat levels (cholesterol and triglycerides). Your healthcare provider will do blood tests to check your lipids before and during treatment. These problems usually go away when ABSORICA or ABSORICA LD treatment is finished.

6.hearing problems. Stop using ABSORICA or ABSORICA LD and call your healthcare provider if your hearing gets worse or if you have ringing in your ears. Your hearing loss may be permanent.

7.liver problems, including hepatitis. Your healthcare provider will do tests to check your liver before and during treatment with ABSORICA or ABSORICA LD. Call your healthcare provider if you get:

8.inflammation of your digestive tract (inflammatory bowel disease). Stop taking ABSORICA or ABSORICA LD and call your healthcare provider if you get:

9.bone and muscle problems. Bone problems include bone pain, softening or thinning (which may lead to fractures). Tell your healthcare provider if you plan hard physical activity during treatment with ABSORICA or ABSORICA LD. Tell your healthcare provider if you get:

10.back pain

11.joint pain or muscle pain

12.broken bone. Tell all healthcare providers that you take ABSORICA or ABSORICA LD if you break a bone.

Stop ABSORICA orABSORICALD and call your healthcare provider right away if you have muscle weakness. Muscle weakness with or without pain can be a sign of serious muscle damage.

ABSORICA and ABSORICA LD may stop long bone growth in teenagers who are still growing.

13.vision problems. Stop taking ABSORICA or ABSORICA LD and call your healthcare provider right away if you have any vision changes. ABSORICA and ABSORICA LD may affect your ability to see in the dark. This usually goes away after you stop taking ABSORICA or ABSORICA LD, but it may be permanent. Some patients get dry eyes during treatment. If you wear contact lenses, you may have trouble wearing them during and after you stop treatment with ABSORICA or ABSORICA LD.

14.serious allergic reactions. Stop taking ABSORICA or ABSORICA LD and get emergency medical help right away if you get hives, a swollen face or mouth, or have trouble breathing. Stop taking ABSORICA or ABSORICA LD and call your healthcare provider if you get a fever, rash, or red patches or bruises on your legs.

15.blood sugar problems, including diabetes. Tell your healthcare provider if you are very thirsty or urinate more than usual.

The most common side effects of ABSORICA and ABSORICALD include:

These are not all of the possible side effects of ABSORICA and ABSORICA LD. Call your doctor for medical advice about side effects. You may report side effects to FDA at 1-800-FDA-1088 or Sun Pharmaceutical Industries, Inc. at 1-800-818-4555.

How should I store ABSORICA and ABSORICALD?

1.Store ABSORICA and ABSORICA LD at room temperature, 68°F to 77°F (20°C to 25°C). Protect from light.

Keep ABSORICA and ABSORICALD and all medicines out of the reach of children.

General Information about the safe and effective use of ABSORICA and ABSORICALD

Medicines are sometimes prescribed for purposes other than those listed in a Medication Guide. Do not use ABSORICA or ABSORICA LD for a condition for which it was not prescribed. Do not give ABSORICA or ABSORICA LD to other people, even if they have the same symptoms that you have. It may harm them. You can ask your healthcare provider or pharmacist for information about ABSORICA and ABSORICA LD that is written for health professionals.

You can also call iPLEDGE Program at 1-866-495-0654 or visit www.ipledgeprogram.com.

What are the ingredients in ABSORICA and ABSORICALD?

Active ingredient: isotretinoin

Inactive ingredients in ABSORICA: propyl gallate, sorbitan monooleate, soybean oil and stearoyl polyoxylglycerides. The gelatin capsules contain the following dye systems:

•10 mg – iron oxide (yellow) and titanium dioxide

•20 mg – iron oxide (red), and titanium dioxide

•25 mg – FD&C Blue #1, FD&C Yellow #5,FD&C Yellow #6 and titanium dioxide

•30 mg – iron oxide (black, red and yellow) and titanium dioxide

•35 mg – FD&C Blue #2, iron oxide (black, red and yellow) and titanium dioxide

•40 mg – iron oxide (black, red and yellow) and titanium dioxide

Inactive ingredients in ABSORICA LD: butylated hydroxy anisole, gelatin, hard gelatin capsule shell, polysorbate 80, and soybean oil. The gelatin capsules contain the following dye systems:

•8 mg – D&C Yellow #10, FD&C Blue #1, FD&C Red #40 and titanium dioxide

•16 mg – FD&C Blue #1, FD&C Red #40, and titanium dioxide

•20 mg – FD&C Blue #1, FD&C Red #40, and titanium dioxide

•24 mg – D&C Yellow #10, FD&C Yellow #6 and titanium dioxide

•28 mg – FD&C Blue #1, FD&C Red #40, and titanium dioxide

•32 mg – ferrosoferric oxide, ferric oxide (red and yellow) and titanium dioxide

The imprinting ink of 8 mg, 16 mg, 24 mg and 32 mg capsules contain the following ingredients: potassium hydroxide, propylene glycol, shellac and titanium dioxide.

The imprinting ink of 20 mg and 28 mg capsules contain the following ingredients: ferrosoferric oxide, propylene glycol and shellac glaze.

ABSORICA LD 8 mg, 16 mg, 20 mg, 24 mg, 28 mg and 32 mg is protected by US Patent No. US 9,700,535 and US 9,750,711.

All trademarks are property of their respective owners.

Distributed by: Sun Pharmaceutical Industries, Inc. Cranbury, NJ 08512

Absorica 25 mg Blister

Contains FD&C Yellow No. 5 (tartrazine) as a color additive.

Each capsule contains 25 mg Isotretinoin, USP

Absorica 25 mg Carton

Contains FD&C Yellow No. 5 (tartrazine) as a color additive.